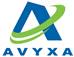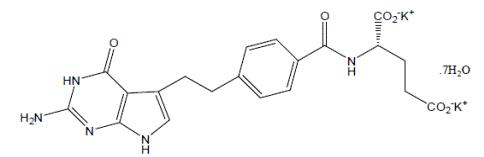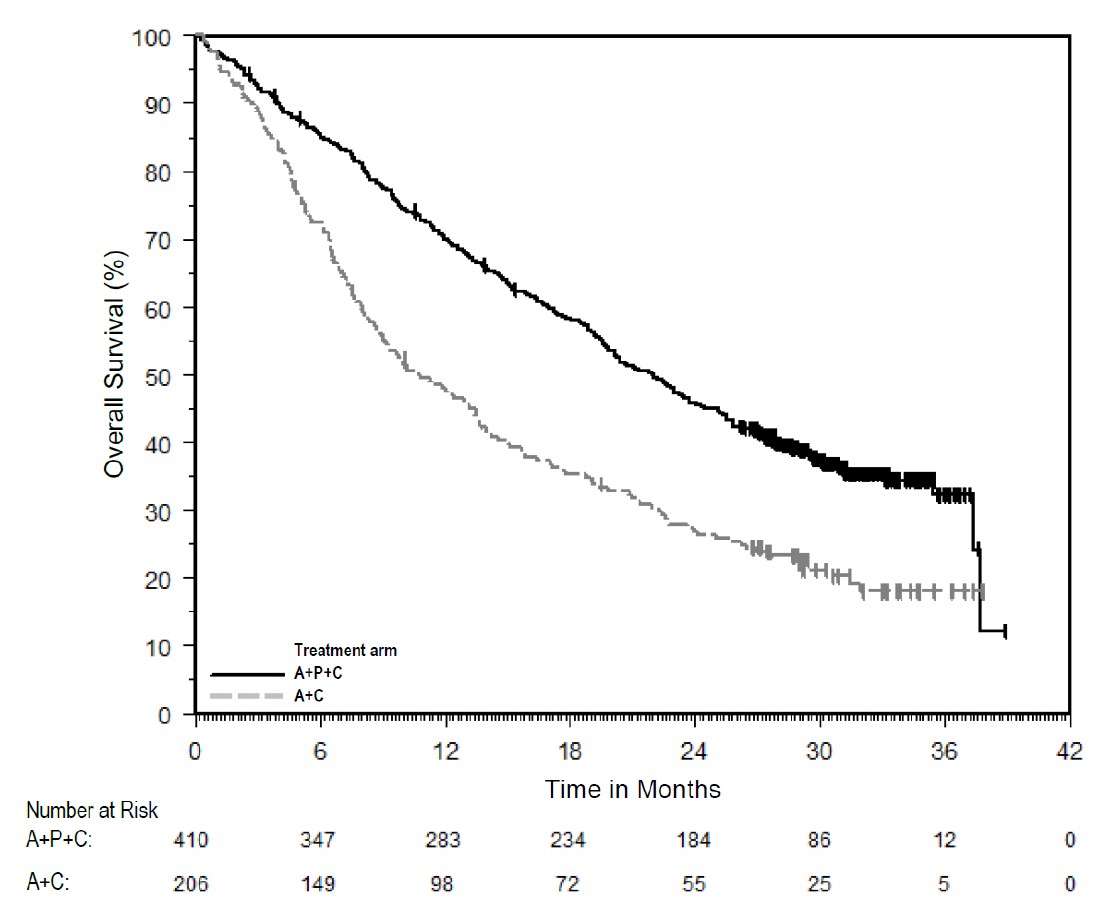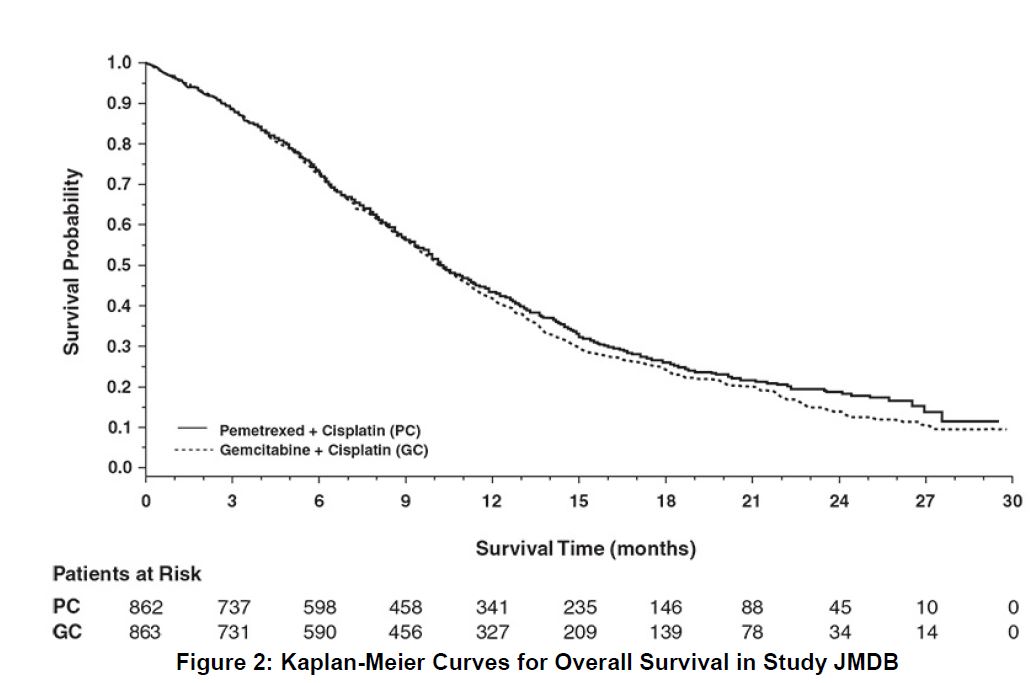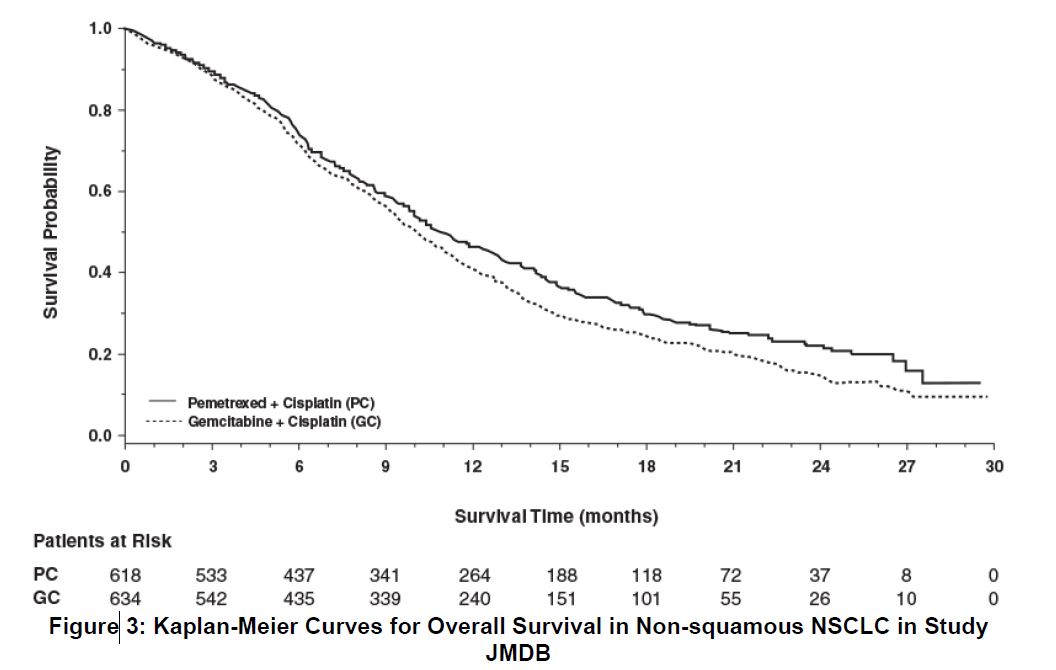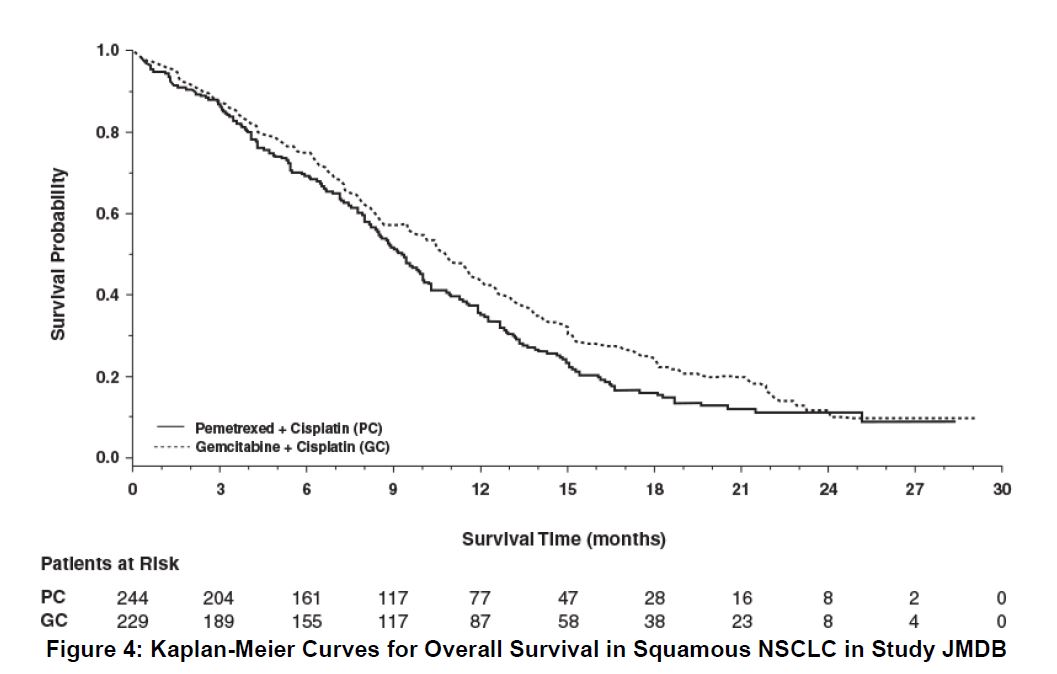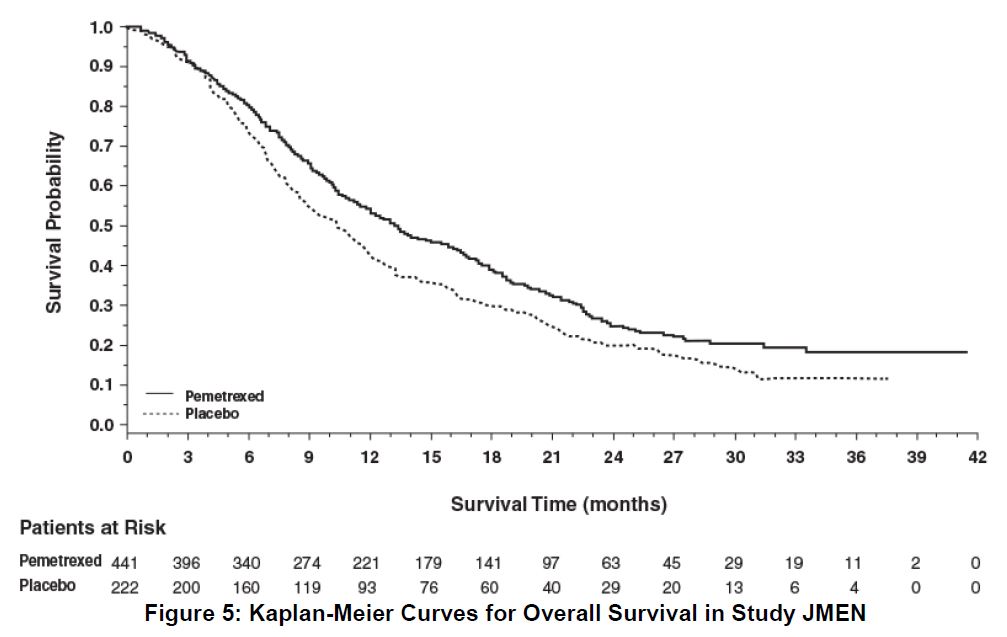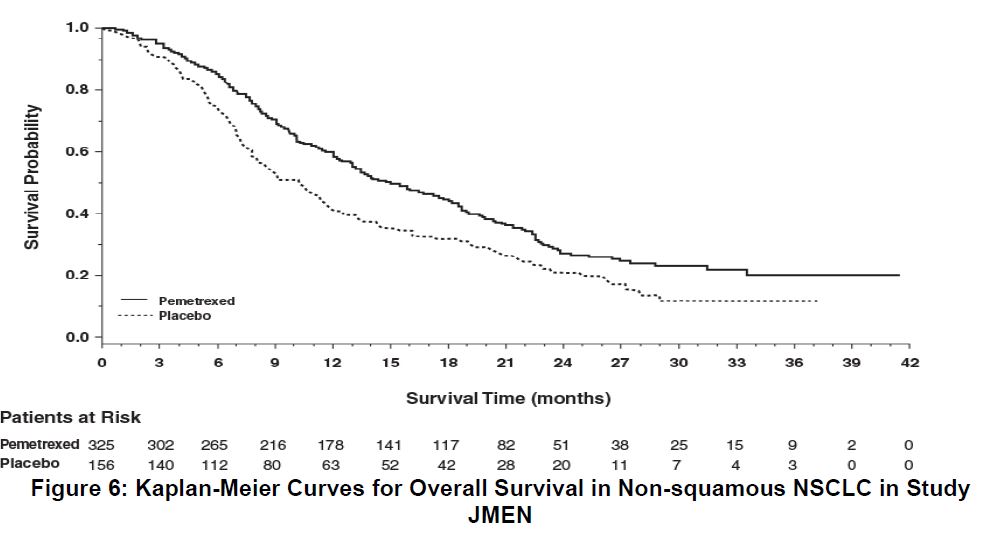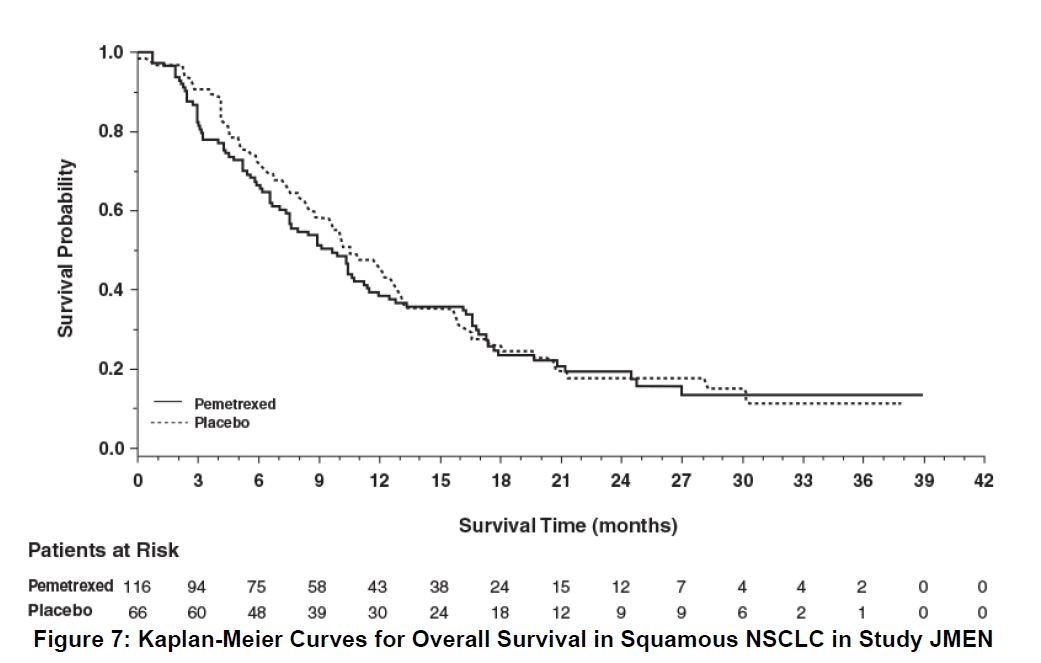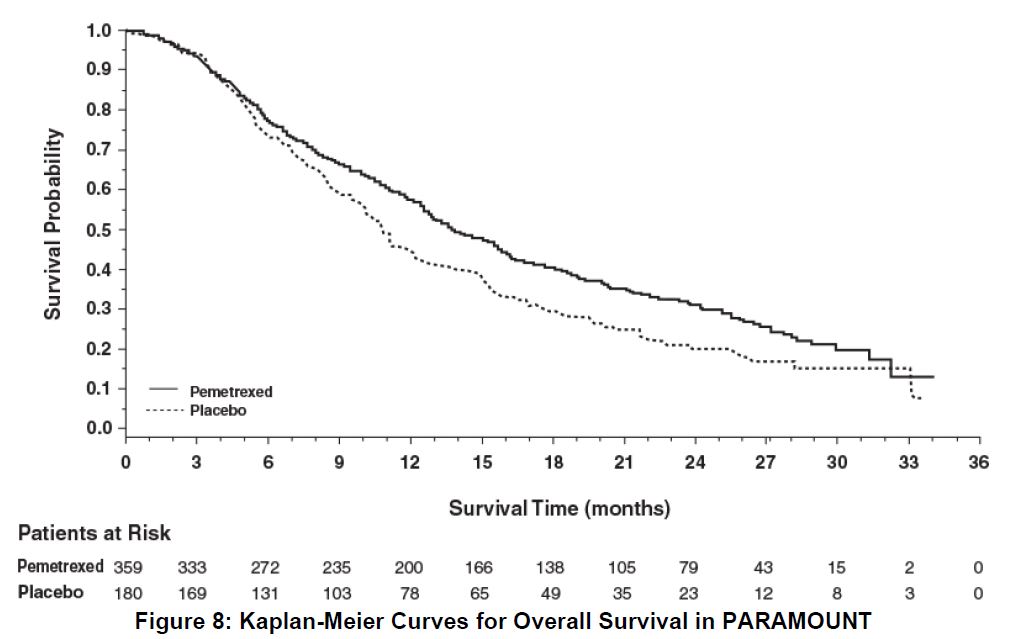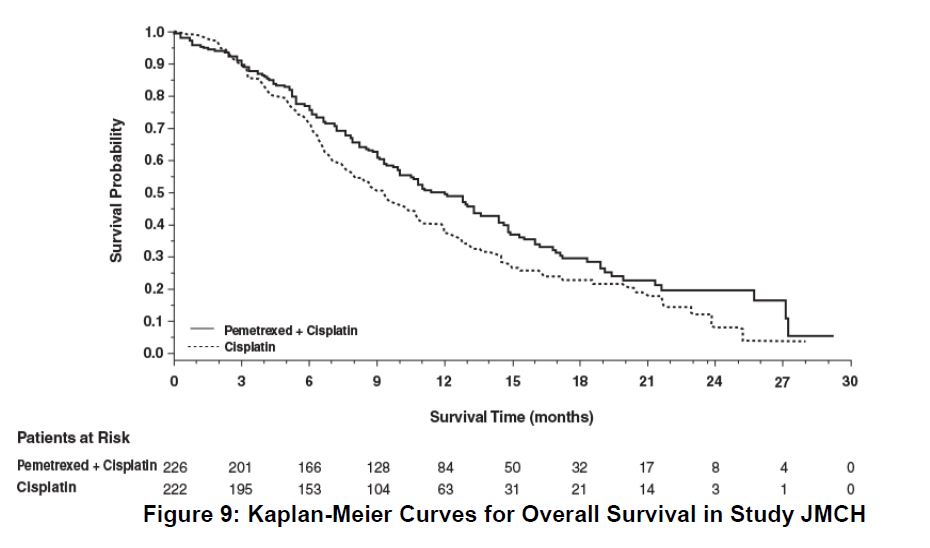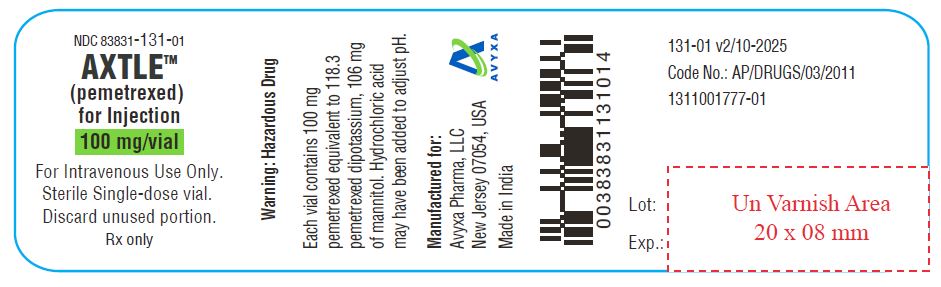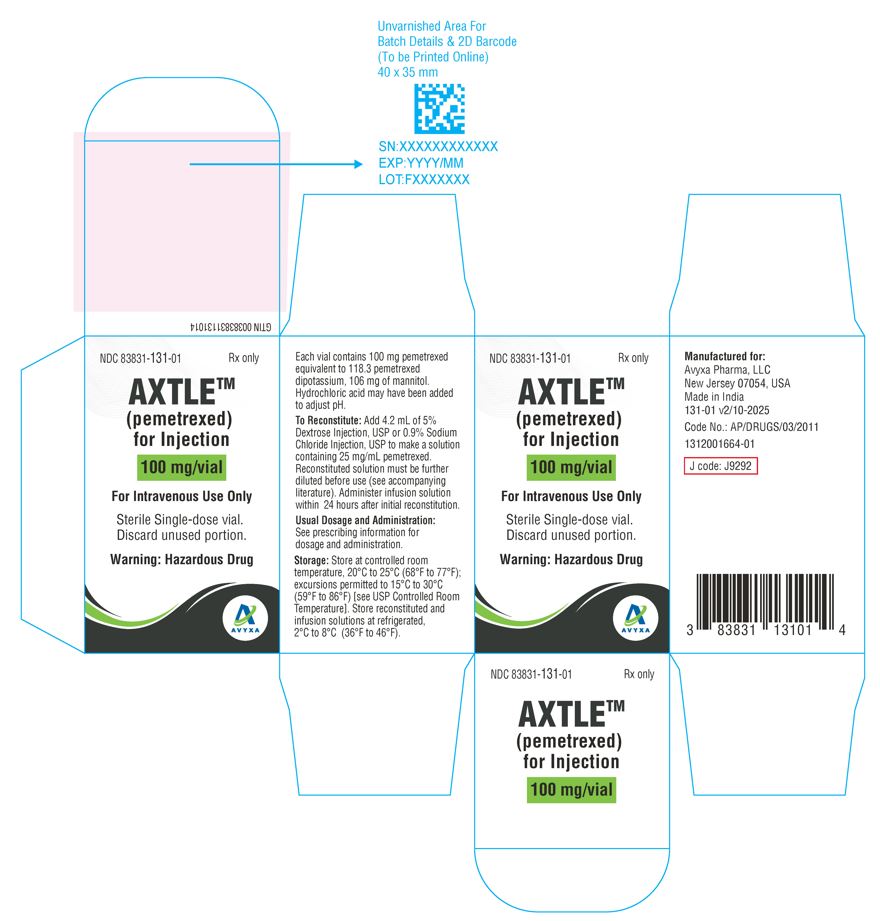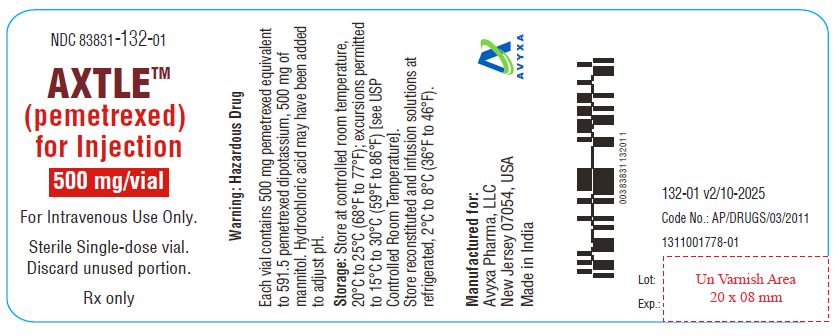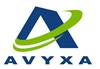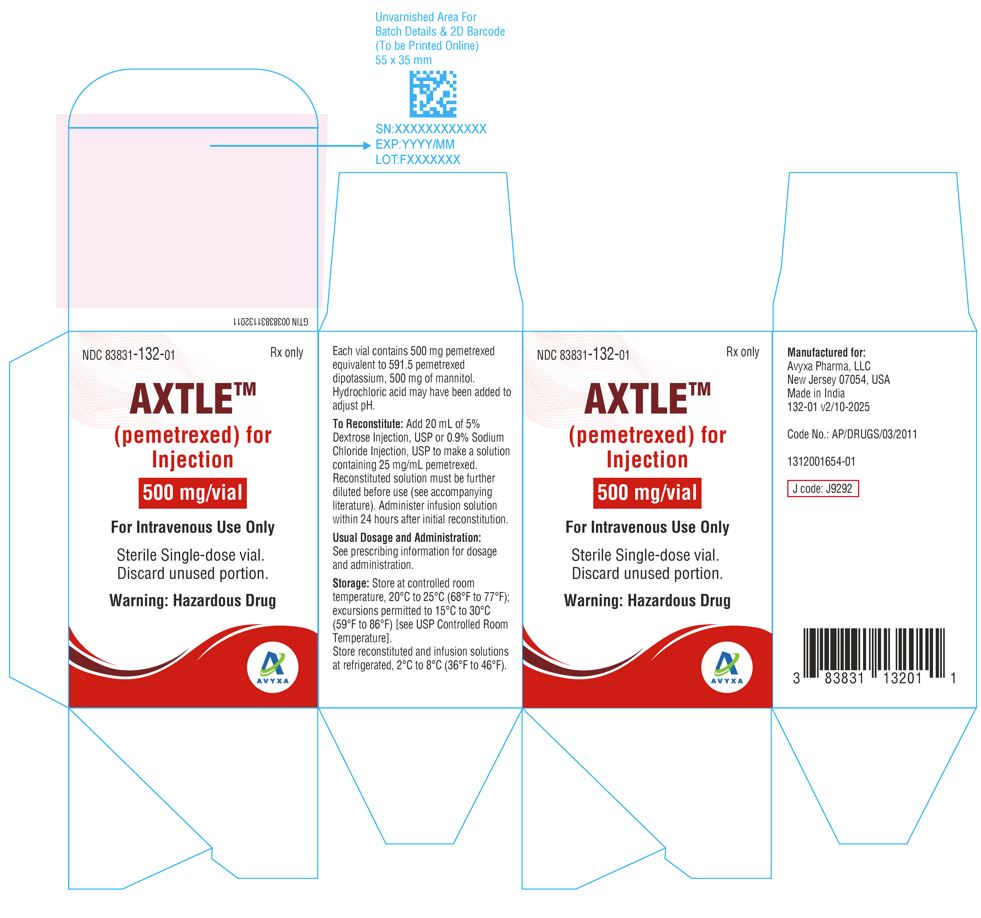 DRUG LABEL: AXTLE
NDC: 83831-131 | Form: INJECTION, POWDER, LYOPHILIZED, FOR SOLUTION
Manufacturer: Avyxa Pharma, LLC
Category: prescription | Type: HUMAN PRESCRIPTION DRUG LABEL
Date: 20251008

ACTIVE INGREDIENTS: PEMETREXED 100 mg/4 mL
INACTIVE INGREDIENTS: MANNITOL; HYDROCHLORIC ACID

HIGHLIGHTS OF PRESCRIBING INFORMATION

These highlights do not include all the information needed to use AXTLE safely and effectively. See full prescribing information for AXTLE.
AXTLETM (pemetrexed) for injection, for intravenous use
Initial U.S. Approval: 2004

RECENT MAJOR CHANGES

Indications and Usage (1.1) 10/2025

Dosage and Administration (2) 10/2025

1 INDICATIONS AND USAGE

AXTLE is a folate analog metabolic inhibitor indicated:

- in combination with pembrolizumab and platinum chemotherapy, for the initial treatment of patients with metastatic non-squamous non-small cell lung cancer (NSCLC), with no EGFR or ALK genomic tumor aberrations. (1.1)
- in combination with cisplatin for the initial treatment of patients with locally advanced or metastatic, non-squamous NSCLC. (1.1)
- as a single agent for the maintenance treatment of patients with locally advanced or metastatic, non-squamous NSCLC whose disease has not progressed after four cycles of platinum-based first-line chemotherapy. (1.1)
- as a single agent for the treatment of patients with recurrent, metastatic non-squamous, NSCLC after prior chemotherapy. (1.1)

Limitations of Use: AXTLE is not indicated for the treatment of patients with squamous cell, non-small cell lung cancer. (1.1)

- initial treatment, in combination with cisplatin, of patients with malignant pleural mesothelioma whose disease is unresectable or who are otherwise not candidates for curative surgery. (1.2)

2 DOSAGE AND ADMINISTRATION

- The recommended dose of AXTLE administered with pembrolizumab and platinum chemotherapy in patients with a creatinine clearance (calculated by Cockcroft-Gault equation) of 45 mL/min or greater is 500 mg/m^2as an intravenous infusion over 10 minutes, administered after pembrolizumab and prior to platinum chemotherapy, on Day 1 of each 21-day cycle. (2.1)
- The recommended dose of AXTLE, administered as a single agent or with cisplatin, in patients with creatinine clearance of 45 mL/minute or greater is 500 mg/m^2as an intravenous infusion over 10 minutes on Day 1 of each 21-day cycle. (2.1, 2.2)
- Initiate folic acid 400 mcg to 1000 mcg orally, once daily, beginning 7 days prior to the first dose of AXTLE and continue until 21 days after the last dose of AXTLE. (2.4)
- Administer vitamin B12, 1 mg intramuscularly, 1 week prior to the first dose of AXTLE and every 3 cycles. (2.4)
- Administer dexamethasone 4 mg orally, twice daily the day before, the day of, and the day after AXTLE administration. (2.4)

3 DOSAGE FORMS AND STRENGTHS

For Injection: 100 mg or 500 mg pemetrexed equivalent to 118.3 mg or 591.5 mg pemetrexed dipotassium as lyophilized powder in single-dose vial (3)

4 CONTRAINDICATIONS

History of severe hypersensitivity reaction to pemetrexed. (4)

5 WARNINGS AND PRECAUTIONS

- Myelosuppression: Can cause severe bone marrow suppression resulting in cytopenia and an increased risk of infection. Do not administer AXTLE when the absolute neutrophil count is less than 1500 cells/mm^3and platelets are less than 100,000 cells/mm^3. Initiate supplementation with oral folic acid and intramuscular vitamin B12to reduce the severity of hematologic and gastrointestinal toxicity of AXTLE. (2.4, 5.1)
- Renal Failure: Can cause severe, and sometimes fatal, renal failure. Do not administer when creatinine clearance is less than 45 mL/min. (2.3, 5.2)
- Bullous and Exfoliative Skin Toxicity: Permanently discontinue for severe and life-threatening bullous, blistering or exfoliating skin toxicity. (5.3)
- Interstitial Pneumonitis: Withhold for acute onset of new or progressive unexplained pulmonary symptoms. Permanently discontinue if pneumonitis is confirmed. (5.4)
- Radiation Recall: Can occur in patients who received radiation weeks to years previously; permanently discontinue for signs of radiation recall. (5.5)
- Embryo-Fetal Toxicity: Can cause fetal harm. Advise patients of the potential risk to a fetus and to use effective contraception. (5.7, 8.1,8.3)

6 ADVERSE REACTIONS

- The most common adverse reactions (incidence ≥20%) of pemetrexed, when administered as a single agent are fatigue, nausea, and anorexia. (6.1)
- The most common adverse reactions (incidence ≥20%) of pemetrexed when administered with cisplatin are vomiting, neutropenia, anemia, stomatitis/pharyngitis, thrombocytopenia, and constipation. (6.1)
- The most common adverse reactions (incidence ≥20%) of pemetrexed when administered in combination with pembrolizumab and platinum chemotherapy are fatigue/asthenia, nausea, constipation, diarrhea, decreased appetite, rash, vomiting, cough, dyspnea, and pyrexia. (6.1)

To report SUSPECTED ADVERSE REACTIONS, contact Avyxa Pharma, LLC at 1-888-520-0954 or FDA at 1-800-FDA-1088 or www.fda.gov/medwatch.

7 DRUG INTERACTIONS

Ibuprofen increased risk of pemetrexed toxicity in patients with mild to moderate renal impairment. Modify the ibuprofen dosage as recommended for patients with a creatinine clearance between 45 mL/min and 79 mL/min. (2.5, 5.6, 7)

8 USE IN SPECIFIC POPULATIONS

Lactation: Advise not to breastfeed. (8.2)

FULL PRESCRIBING INFORMATION

1 INDICATIONS AND USAGE

1.1 Non-Squamous Non-Small Cell Lung Cancer (NSCLC)

AXTLE is indicated:

- in combination with pembrolizumab and platinum chemotherapy, for the initial treatment of patients with metastatic non-squamous non-small cell lung cancer (NSCLC), with no EGFR or ALK genomic tumor aberrations.

- in combination with cisplatin for the initial treatment of patients with locally advanced or metastatic, non-squamous NSCLC.
- as a single agent for the maintenance treatment of patients with locally advanced or metastatic, non-squamous NSCLC whose disease has not progressed after four cycles of platinum-based first-line chemotherapy.
- as a single agent for the treatment of patients with recurrent, metastatic non-squamous, NSCLC after prior chemotherapy.

Limitations of Use: AXTLE is not indicated for the treatment of patients with squamous cell, non-small cell lung cancer [see Clinical Studies (14.1)].

● initial treatment, in combination with cisplatin, of patients with malignant pleural mesothelioma whose disease is unresectable or who are otherwise not candidates for curative surgery. (1.2)

1.2 Mesothelioma

AXTLE is indicated, in combination with cisplatin, for the initial treatment of patients with malignant pleural mesothelioma whose disease is unresectable or who are otherwise not candidates for curative surgery.

2 DOSAGE AND ADMINISTRATION

2.1 Recommended Dosage for Non-Squamous NSCLC

- The recommended dose of AXTLE when administered with pembrolizumab and platinum chemotherapy for the initial treatment of metastatic non-squamous NSCLC in patients with a creatinine clearance (calculated by Cockcroft-Gault equation) of 45 mL/min or greater is 500 mg/m^2as an intravenous infusion over 10 minutes administered after pembrolizumab and prior to carboplatin or cisplatin on Day 1 of each 21-day cycle for 4 cycles. Following completion of platinum-based therapy, treatment with AXTLE with or without pembrolizumab is administered until disease progression or unacceptable toxicity. Please refer to the full prescribing information for pembrolizumab and for carboplatin or cisplatin.

- The recommended dose of AXTLE when administered with cisplatin for initial treatment of locally advanced or metastatic non-squamous NSCLC in patients with a creatinine clearance (calculated by Cockcroft-Gault equation) of 45 mL/min or greater is 500 mg/m^2as an intravenous infusion over 10 minutes administered prior to cisplatin on Day 1 of each 21-day cycle for up to six cycles in the absence of disease progression or unacceptable toxicity.
- The recommended dose of AXTLE for maintenance treatment of non-squamous NSCLC in patients with a creatinine clearance (calculated by Cockcroft-Gault equation) of 45 mL/min or greater is 500 mg/m^2as an intravenous infusion over 10 minutes on Day 1 of each 21-day cycle until disease progression or unacceptable toxicity after four cycles of platinum-based first-line chemotherapy.
- The recommended dose of AXTLE for treatment of recurrent non-squamous NSCLC in patients with a creatinine clearance (calculated by Cockcroft-Gault equation) of 45 mL/min or greater is 500 mg/m^2as an intravenous infusion over 10 minutes on Day 1 of each 21-day cycle until disease progression or unacceptable toxicity.

2.2 Recommended Dosage for Mesothelioma

- The recommended dose of AXTLE when administered with cisplatin in patients with a creatinine clearance (calculated by Cockcroft-Gault equation) of 45 mL/min or greater is 500 mg/m^2as an intravenous infusion over 10 minutes on Day 1 of each 21-day cycle until disease progression or unacceptable toxicity.

2.3 Renal Impairment

- AXTLE dosing recommendations are provided for patients with a creatinine clearance (calculated by Cockcroft-Gault equation) of 45 mL/min or greater [see Dosage and Administration (2.1,2.2)]. There is no recommended dose for patients whose creatinine clearance is less than 45 mL/min [see Use in Specific Populations (8.6)].

2.4 Premedication and Concomitant Medications to Mitigate Toxicity

Vitamin Supplementation

- Initiate folic acid 400 mcg to 1000 mcg orally once daily, beginning 7 days before the first dose of AXTLE and continuing until 21 days after the last dose of AXTLE [see Warnings and Precautions (5.1)].
- Administer vitamin B12,1 mg intramuscularly, 1 week prior to the first dose of AXTLE and every 3 cycles thereafter. Subsequent vitamin B12injections may be given the same day as treatment with AXTLE[see Warnings and Precautions (5.1)]. Do not substitute oral vitamin B12for intramuscular vitamin B12.

Corticosteroids

- Administer dexamethasone 4 mg orally twice daily for three consecutive days, beginning the day before each AXTLE administration.

2.5 Dosage Modification of Ibuprofen in Patients with Mild to Moderate Renal Impairment Receiving AXTLE

In patients with creatinine clearances between 45 mL/min and 79 mL/min, modify administration of ibuprofen as follows [see Warnings and Precautions (5.6), Drug Interactions (7) and Clinical Pharmacology (12.3)]:

- Avoid administration of ibuprofen for 2 days before, the day of, and 2 days following administration of AXTLE.
- Monitor patients more frequently for myelosuppression, renal, and gastrointestinal toxicity, if concomitant administration of ibuprofen cannot be avoided.

2.6 Dosage Modifications for Adverse Reactions

Obtain complete blood count on Days 1, 8, and 15 of each cycle. Assess creatinine clearance prior to each cycle. Do not administer AXTLE if the creatinine clearance is less than 45 mL/min.

Delay initiation of the next cycle of AXTLE until:

- recovery of non-hematologic toxicity to Grade 0-2,
- absolute neutrophil count (ANC) is 1500 cells/mm^3or higher, and
- platelet count is 100,000 cells/mm^3or higher.

Upon recovery, modify the dosage of AXTLE in the next cycle as specified in Table 1.
For dosing modifications for cisplatin, carboplatin, or pembrolizumab, refer to their prescribing information.

Table 1: Recommended Dosage Modifications for Adverse Reactionsa
Toxicity in Most Recent Treatment Cycle | AXTLE Dose Modification for Next Cycle
Myelosuppressive toxicity [see Warnings and Precautions (5.1)]
ANC less than 500/mm^3 and platelets greater than or equal to 50,000/mm^3 OR Platelet count less than 50,000/mm^3 without bleeding. | 75% of previous dose
Platelet count less than 50,000/mm^3 with bleeding | 50% of previous dose
Recurrent Grade 3 or 4 myelosuppression after 2 dose reductions | Discontinue
Non-hematologic toxicity
Any Grade 3 or 4 toxicities EXCEPT mucositis or neurologic toxicity OR Diarrhea requiring hospitalization | 75% of previous dose
Grade 3 or 4 mucositis | 50% of previous dose
Renal toxicity [see Warnings and Precautions (5.2)] | Withhold until creatinine clearance is 45 mL/min or greater
Grade 3 or 4 neurologic toxicity | Permanently discontinue
Recurrent Grade 3 or 4 non-hematologic toxicity after 2 dose reductions | Permanently discontinue
Severe and life-threatening Skin Toxicity [see Warnings and Precautions (5.3)] | Permanently discontinue
Interstitial Pneumonitis [see Warnings and Precautions (5.4)] | Permanently discontinue
a National Cancer Institute Common Toxicity Criteria for Adverse Events version 2 (NCI CTCAE v2).

2.7 Preparation for Administration

- AXTLE is a hazardous drug. Follow applicable special handling and disposal procedures.^1

- Calculate the dose of AXTLE and determine the number of vials needed.

- Reconstitute AXTLE to achieve a concentration of 25 mg/mL as follows:

- Reconstitute each 100-mg vial with 4.2 mL of 5% Dextrose Injection, USP (preservative-free) or 0.9% Sodium Chloride Injection, USP (preservative-free)
- Reconstitute each 500-mg vial with 20 mL of 5% Dextrose Injection, USP (preservative-free) or 0.9% Sodium Chloride Injection, USP (preservative-free)
- Do not use calcium-containing solutions for reconstitution.

- Gently swirl each vial until the powder is completely dissolved. The resulting solution is clear and ranges in color from colorless to yellow or green-yellow. FURTHER DILUTION IS REQUIRED prior to administration.
- Store reconstituted, preservative-free product under refrigerated conditions [2-8°C (36-46°F)] for no longer than 24 hours from the time of reconstitution. Discard vial after 24 hours.
- Inspect reconstituted product visually for particulate matter and discoloration prior to further dilution. If particulate matter is observed, discard vial.
- Withdraw the calculated dose of AXTLE from the vial(s) and discard vial with any unused portion.

- Further dilute AXTLE with 5% Dextrose Injection, USP or 0.9% Sodium Chloride Injection, USP to achieve a total volume of 100 mL for intravenous infusion.

- Store diluted, reconstituted product under refrigerated conditions [2-8°C (36-46°F)] for no more than 24 hours from the time of reconstitution. Discard after 24 hours.

3 DOSAGE FORMS AND STRENGTHS

For injection: 100 mg or 500 mg pemetrexed equivalent to 118.3 mg or 591.5 mg pemetrexed dipotassium as a sterile preservative free white to light-yellow or green-yellow lyophilized powder in single-dose vials for reconstitution.

4 CONTRAINDICATIONS

AXTLE is contraindicated in patients with a history of severe hypersensitivity reaction to pemetrexed [see Adverse Reactions (6.1)].

5 WARNINGS AND PRECAUTIONS

5.1 Myelosuppression and Increased Risk of Myelosuppression without Vitamin Supplementation

AXTLE can cause severe myelosuppression resulting in a requirement for transfusions and which may lead to neutropenic infection. The risk of myelosuppression is increased in patients who do not receive vitamin supplementation. In Study JMCH, incidences of Grade 3-4 neutropenia (38% versus 23%), thrombocytopenia (9% versus 5%), febrile neutropenia (9% versus 0.6%), and neutropenic infection (6% versus 0) were higher in patients who received pemetrexed plus cisplatin without vitamin supplementation as compared to patients who were fully supplemented with folic acid and vitamin B12 prior to and throughout pemetrexed plus cisplatin treatment.

Initiate supplementation with oral folic acid and intramuscular vitamin B12 prior to the first dose of AXTLE; continue vitamin supplementation during treatment and for 21 days after the last dose of AXTLE to reduce the severity of hematologic and gastrointestinal toxicity of AXTLE [see Dosage and Administration (2.4)]. Obtain a complete blood count at the beginning of each cycle. Do not administer AXTLE until the ANC is at least 1500 cells/mm^3 and platelet count is at least 100,000 cells/mm^3. Permanently reduce AXTLE in patients with an ANC of less than 500 cells/mm^3 or platelet count of less than 50,000 cells/mm^3 in previous cycles [see Dosage and Administration (2.6)].

In Studies JMDB and JMCH, among patients who received vitamin supplementation, incidence of Grade 3-4 neutropenia was 15% and 23%, the incidence of Grade 3-4 anemia was 6% and 4%, and incidence of Grade 3-4 thrombocytopenia was 4% and 5%, respectively. In Study JMCH, 18% of patients in the pemetrexed arm required red blood cell transfusions compared to 7% of patients in the cisplatin arm [see Adverse Reactions (6.1)]. In Studies JMEN, PARAMOUNT, and JMEI, where all patients received vitamin supplementation, incidence of Grade 3-4 neutropenia ranged from 3% to 5%, and incidence of Grade 3-4 anemia ranged from 3% to 5%.

5.2 Renal Failure

AXTLE can cause severe, and sometimes fatal, renal toxicity. The incidences of renal failure in clinical studies in which patients received pemetrexed with cisplatin were: 2.1% in Study JMDB and 2.2% in Study JMCH. The incidence of renal failure in clinical studies in which patients received pemetrexed as a single agent ranged from 0.4% to 0.6% (Studies JMEN, PARAMOUNT, and JMEI [see Adverse Reactions (6.1)]. Determine creatinine clearance before each dose and periodically monitor renal function during treatment with AXTLE. Withhold AXTLE in patients with a creatinine clearance of less than 45 mL/minute [see Dosage and Administration (2.3)].

5.3 Bullous and Exfoliative Skin Toxicity

Serious and sometimes fatal, bullous, blistering and exfoliative skin toxicity, including cases suggestive of Stevens-Johnson Syndrome/Toxic epidermal necrolysis can occur with AXTLE. Permanently discontinue AXTLE for severe and life-threatening bullous, blistering or exfoliating skin toxicity.

5.4 Interstitial Pneumonitis

Serious interstitial pneumonitis, including fatal cases, can occur with AXTLE treatment. Withhold AXTLE for acute onset of new or progressive unexplained pulmonary symptoms such as dyspnea, cough, or fever pending diagnostic evaluation. If pneumonitis is confirmed, permanently discontinue AXTLE.

5.5 Radiation Recall

Radiation recall can occur with AXTLE in patients who have received radiation weeks to years previously. Monitor patients for inflammation or blistering in areas of previous radiation treatment. Permanently discontinue AXTLE for signs of radiation recall.

5.6 Increased Risk of Toxicity with Ibuprofen in Patients with Renal Impairment

Exposure to pemetrexed is increased in patients with mild to moderate renal impairment who take concomitant ibuprofen, increasing the risks of adverse reactions of AXTLE. In patients with creatinine clearances between 45 mL/min and 79 mL/min, avoid administration of ibuprofen for 2 days before, the day of, and 2 days following administration of AXTLE. If concomitant ibuprofen use cannot be avoided, monitor patients more frequently for pemetrexed adverse reactions, including myelosuppression, renal, and gastrointestinal toxicity [see Dosage and Administration (2.5), Drug Interactions (7), and Clinical Pharmacology (12.3)].

5.7 Embryo-Fetal Toxicity

Based on findings from animal studies and its mechanism of action, AXTLE can cause fetal harm when administered to a pregnant woman. In animal reproduction studies, intravenous administration of pemetrexed to pregnant mice during the period of organogenesis was teratogenic, resulting in developmental delays and increased malformations at doses lower than the recommended human dose of 500 mg/m^2. Advise pregnant women of the potential risk to a fetus. Advise females of reproductive potential to use effective contraception during treatment with AXTLE and for 6 months after the last dose. Advise males with female partners of reproductive potential to use effective contraception during treatment with AXTLE and for 3 months after the last dose [see Use in Specific Populations (8.1, 8.3) and Clinical Pharmacology (12.1)].

6 ADVERSE REACTIONS

The following adverse reactions are discussed in greater detail in other sections of the labeling:

- Myelosuppression [see Warnings and Precautions (5.1)]
- Renal failure [see Warnings and Precautions (5.2)]
- Bullous and exfoliative skin toxicity [see Warnings and Precautions (5.3)]
- Interstitial pneumonitis [see Warnings and Precautions (5.4)]
- Radiation recall [see Warnings and Precautions (5.5)]

6.1 Clinical Trials Experience

Because clinical trials are conducted under widely varying conditions, adverse reactions rates cannot be directly compared to rates in other clinical trials and may not reflect the rates observed in clinical practice.

In clinical trials, the most common adverse reactions (incidence ≥20%) of pemetrexed, when administered as a single agent, are fatigue, nausea, and anorexia. The most common adverse reactions (incidence ≥20%) of pemetrexed, when administered in combination with cisplatin are vomiting, neutropenia, anemia, stomatitis/pharyngitis, thrombocytopenia, and constipation. The most common adverse reactions (incidence ≥20%) of pemetrexed, when administered in combination with pembrolizumab and platinum chemotherapy, are fatigue/asthenia, nausea, constipation, diarrhea, decreased appetite, rash, vomiting, cough, dyspnea, and pyrexia.

Non-Squamous NSCLC

First-line Treatment of Metastatic Non-squamous NSCLC with Pembrolizumab and Platinum Chemotherapy

The safety of pemetrexed, in combination with pembrolizumab and investigator's choice of platinum (either carboplatin or cisplatin), was investigated in Study KEYNOTE-189, a multicenter, double-blind, randomized (2:1), active-controlled trial in patients with previously untreated, metastatic non-squamous NSCLC with no EGFR or ALK genomic tumor aberrations. A total of 607 patients received pemetrexed, pembrolizumab, and platinum every 3 weeks for 4 cycles followed by pemetrexed and pembrolizumab (n=405), or placebo, pemetrexed, and platinum every 3 weeks for 4 cycles followed by placebo and pemetrexed (n=202). Patients with autoimmune disease that required systemic therapy within 2 years of treatment; a medical condition that required immunosuppression; or who had received more than 30 Gy of thoracic radiation within the prior 26 weeks were ineligible [see Clinical Studies (14.1)].

The median duration of exposure to pemetrexed was 7.2 months (range: 1 day to 1.7 years). Seventy-two percent of patients received carboplatin. The study population characteristics were: median age of 64 years (range: 34 to 84), 49% age 65 years or older, 59% male, 94% White and 3% Asian, and 18% with history of brain metastases at baseline.

Pemetrexed was discontinued for adverse reactions in 23% of patients in the pemetrexed, pembrolizumab, and platinum arm. The most common adverse reactions resulting in discontinuation of pemetrexed in this arm were acute kidney injury (3%) and pneumonitis (2%). Adverse reactions leading to interruption of pemetrexed occurred in 49% of patients in the pemetrexed, pembrolizumab, and platinum arm. The most common adverse reactions or laboratory abnormalities leading to interruption of pemetrexed in this arm (≥2%) were neutropenia (12%), anemia (7%), asthenia (4%), pneumonia (4%), thrombocytopenia (4%), increased blood creatinine (3%), diarrhea (3%), and fatigue (3%).

Table 2 summarizes the adverse reactions that occurred in ≥20% of patients treated with pemetrexed, pembrolizumab, and platinum.

Table 2: Adverse Reactions Occurring in ≥20% of Patients in KEYNOTE-189
 | Pemetrexed Pembrolizumab Platinum Chemotherapy n=405 |  | Placebo Pemetrexed Platinum Chemotherapy n=202
Adverse Reaction | All Gradesa (%) | Grade 3-4 (%) | All Grades (%) | Grade 3-4 (%)
Gastrointestinal Disorders
Nausea | 56 | 3.5 | 52 | 3.5
Constipation | 35 | 1.0 | 32 | 0.5
Diarrhea | 31 | 5 | 21 | 3.0
Vomiting | 24 | 3.7 | 23 | 3.0
General Disorders and Administration Site Conditions
Fatigueb | 56 | 12 | 58 | 6
Pyrexia | 20 | 0.2 | 15 | 0
Metabolism and Nutrition Disorders
Decreased appetite | 28 | 1.5 | 30 | 0.5
Skin and Subcutaneous Tissue Disorders
Rashc | 25 | 2.0 | 17 | 2.5
Respiratory, Thoracic and Mediastinal Disorders
Cough | 21 | 0 | 28 | 0
Dyspnea | 21 | 3.7 | 26 | 5
a Graded per NCI CTCAE version 4.03.
b Includes asthenia and fatigue.
c Includes genital rash, rash, rash generalized, rash macular, rash maculo-papular, rash papular, rash pruritic, and rash pustular.

Table 3 summarizes the laboratory abnormalities that worsened from baseline in at least 20% of patients treated with pemetrexed, pembrolizumab, and platinum.

Table 3: Laboratory Abnormalities Worsened from Baseline in ≥20% of Patients in KEYNOTE-189
 | Pemetrexed Pembrolizumab Platinum Chemotherapy |  | Placebo Pemetrexed Platinum Chemotherapy
Laboratory Testa | All Gradesb % | Grades 3-4 % | Laboratory Testa | All Gradesb %
Chemistry
Hyperglycemia | 63 | 9 | 60 | 7
Increased ALT | 47 | 3.8 | 42 | 2.6
Increased AST | 47 | 2.8 | 40 | 1.0
Hypoalbuminemia | 39 | 2.8 | 39 | 1.1
Increased creatinine | 37 | 4.2 | 25 | 1.0
Hyponatremia | 32 | 7 | 23 | 6
Hypophosphatemia | 30 | 10 | 28 | 14
Increased alkaline phosphatase | 26 | 1.8 | 29 | 2.1
Hypocalcemia | 24 | 2.8 | 17 | 0.5
Hyperkalemia | 24 | 2.8 | 19 | 3.1
Hypokalemia | 21 | 5 | 20 | 5
Hematology
Anemia | 85 | 17 | 81 | 18
Lymphopenia | 64 | 22 | 64 | 25
Neutropenia | 48 | 20 | 41 | 19
Thrombocytopenia | 30 | 12 | 29 | 8
a Each test incidence is based on the number of patients who had both baseline and at least one on-study laboratory measurement available: pemetrexed /pembrolizumab/platinum chemotherapy (range: 381 to 401 patients) and placebo/ pemetrexed /platinum chemotherapy (range: 184 to 197 patients).
b Graded per NCI CTCAE version 4.03.

Initial Treatment in Combination with Cisplatin

The safety of pemetrexed was evaluated in Study JMDB, a randomized (1:1), open-label, multicenter trial conducted in chemotherapy-naive patients with locally advanced or metastatic NSCLC. Patients received either pemetrexed 500 mg/m^2intravenously and cisplatin 75 mg/m^2intravenously on Day 1 of each 21-day cycle (n=839) or gemcitabine 1250 mg/m^2intravenously on Days 1 and 8 and cisplatin 75 mg/m^2intravenously on Day 1 of each 21-day cycle (n=830). All patients were fully supplemented with folic acid and vitamin B12.

Study JMDB excluded patients with an Eastern Cooperative Oncology Group Performance Status (ECOG PS of 2 or greater), uncontrolled third-space fluid retention, inadequate bone marrow reserve and organ function, or a calculated creatinine clearance less than 45 mL/min. Patients unable to stop using aspirin or other non-steroidal anti-inflammatory drugs or unable to take folic acid, vitamin B12 or corticosteroids were also excluded from the study.

The data described below reflect exposure to pemetrexed plus cisplatin in 839 patients in Study JMDB. Median age was 61 years (range 26-83 years); 70% of patients were men; 78% were White,16% were Asian, 2.9% were Hispanic or Latino, 2.1% were Black or African American, and <1% were other ethnicities; 36% had an ECOG PS 0. Patients received a median of 5 cycles of pemetrexed.

Table 4 provides the frequency and severity of adverse reactions that occurred in ≥5% of 839 patients receiving pemetrexed in combination with cisplatin in Study JMDB. Study JMDB was not designed to demonstrate a statistically significant reduction in adverse reaction rates for pemetrexed, as compared to the control arm, for any specified adverse reaction listed in Table 4

Table 4: Adverse Reactions Occurring in ≥5% of Fully Vitamin-Supplemented Patients Receiving Pemetrexed in Combination with Cisplatin Chemotherapy in Study JMDB
Adverse Reactiona | Pemetrexed/Cisplatin (N=839) |  | Gemcitabine/Cisplatin (N=830)
Adverse Reactiona | All Grades (%) | Grade 3-4 (%) | All Grades (%) | Grade 3-4 (%)
All adverse reactions | 90 | 37 | 91 | 53
Laboratory
Hematologic
Anemia | 33 | 6 | 46 | 10
Neutropenia | 29 | 15 | 38 | 27
Thrombocytopenia | 10 | 4 | 27 | 13
Renal
Elevated creatinine | 10 | 1 | 7 | 1
Clinical
Constitutional symptoms
Fatigue | 43 | 7 | 45 | 5
Gastrointestinal
Nausea | 56 | 7 | 53 | 4
Vomiting | 40 | 6 | 36 | 6
Anorexia | 27 | 2 | 24 | 1
Constipation | 21 | 1 | 20 | 0
Stomatitis/pharyngitis | 14 | 1 | 12 | 0
Diarrhea | 12 | 1 | 13 | 2
Dyspepsia/heartburn | 5 | 0 | 6 | 0
Neurology
Sensory neuropathy | 9 | 0 | 12 | 1
Taste disturbance | 8 | 0 | 9 | 0
Dermatology/Skin
Alopecia | 12 | 0 | 21 | 1
Rash/Desquamation | 7 | 0 | 8 | 1
a NCI CTCAE version 2.0.

The following additional adverse reactions of pemetrexed were observed.

Incidence 1% to <5%

Body as a Whole — febrile neutropenia, infection, pyrexia

General Disorders — dehydration

Metabolism and Nutrition — increased AST, increased ALT

Renal — renal failure

Eye Disorder — conjunctivitis

Incidence <1%

Cardiovascular — arrhythmia

General Disorders — chest pain

Metabolism and Nutrition — increased GGT

Neurology — motor neuropathy

Maintenance Treatment Following First-line Non-Pemetrexed Containing Platinum-Based Chemotherapy

In Study JMEN, the safety of pemetrexed was evaluated in a randomized (2:1), placebo-controlled, multicenter trial conducted in patients with non-progressive locally advanced or metastatic NSCLC following four cycles of a first-line, platinum-based chemotherapy regimen. Patients received either pemetrexed 500 mg/m^2or matching placebo intravenously every 21 days until disease progression or unacceptable toxicity. Patients in both study arms were fully supplemented with folic acid and vitamin B12.

Study JMEN excluded patients with an ECOG PS of 2 or greater, uncontrolled third-space fluid retention, inadequate bone marrow reserve and organ function, or a calculated creatinine clearance less than 45 mL/min. Patients unable to stop using aspirin or other non-steroidal anti-inflammatory drugs or unable to take folic acid, vitamin B12 or corticosteroids were also excluded from the study.

The data described below reflect exposure to pemetrexed in 438 patients in Study JMEN. Median age was 61 years (range 26-83 years), 73% of patients were men; 65% were White, 31% were Asian, 2.9% were Hispanic or Latino, and <2% were other ethnicities; 39% had an ECOG PS 0. Patients received a median of 5 cycles of pemetrexed and a relative dose intensity of pemetrexed of 96%. Approximately half the patients (48%) completed at least six, 21-day cycles and 23% completed ten or more 21-day cycles of pemetrexed.

Table 5 provides the frequency and severity of adverse reactions reported in ≥5% of the 438 pemetrexed-treated patients in Study JMEN.

Table 5: Adverse Reactions Occurring in ≥5% of Patients Receiving Pemetrexed in Study JMEN
Adverse Reactiona | Pemetrexed (N=438) |  | Placebo (N=218)
Adverse Reactiona | All Grades (%) | Grade 3-4 (%) | All Grades (%) | Grade 3-4 (%)
All adverse reactions | 66 | 16 | 37 | 4
Laboratory
Hematologic
Anemia | 15 | 3 | 6 | 1
Neutropenia | 6 | 3 | 0 | 0
Hepatic
Increased ALT | 10 | 0 | 4 | 0
Increased AST | 8 | 0 | 4 | 0
Clinical
Constitutional symptoms
Fatigue | 25 | 5 | 11 | 1
Gastrointestinal
Nausea | 19 | 1 | 6 | 1
Anorexia | 19 | 2 | 5 | 0
Vomiting | 9 | 0 | 1 | 0
Mucositis/stomatitis | 7 | 1 | 2 | 0
Diarrhea | 5 | 1 | 3 | 0
Infection | 5 | 2 | 2 | 0
Neurology
Sensory neuropathy | 9 | 1 | 4 | 0
Dermatology/Skin
Rash/desquamation | 10 | 0 | 3 | 0
a NCI CTCAE version 3.0.

The requirement for transfusions (9.5% versus 3.2%), primarily red blood cell transfusions, and for erythropoiesis stimulating agents (5.9% versus 1.8%) were higher in the pemetrexed arm compared to the placebo arm.

The following additional adverse reactions were observed in patients who received pemetrexed.

Incidence 1% to <5%

Dermatology/Skin — alopecia, pruritus/itching

Gastrointestinal — constipation

General Disorders — edema, fever

Hematologic — thrombocytopenia

Eye Disorder — ocular surface disease (including conjunctivitis), increased lacrimation

Incidence <1%

Cardiovascular — supraventricular arrhythmia

Dermatology/Skin — erythema multiforme

General Disorders — febrile neutropenia, allergic reaction/hypersensitivity

Neurology — motor neuropathy

Renal — renal failure

Maintenance Treatment Following First-line Pemetrexed Plus Platinum Chemotherapy

The safety of pemetrexed was evaluated in PARAMOUNT, a randomized (2:1), placebo-controlled study conducted in patients with non-squamous NSCLC with non-progressive (stable or responding disease) locally advanced or metastatic NSCLC following four cycles of pemetrexed in combination with cisplatin as first-line therapy for NSCLC. Patients were randomized to receive pemetrexed 500 mg/m^2or matching placebo intravenously on Day 1 of each 21-day cycle until disease progression or unacceptable toxicity. Patients in both study arms received folic acid and vitamin B12 supplementation.

PARAMOUNT excluded patients with an ECOG PS of 2 or greater, uncontrolled third-space fluid retention, inadequate bone marrow reserve and organ function, or a calculated creatinine clearance less than 45 mL/min. Patients unable to stop using aspirin or other non-steroidal anti-inflammatory drugs or unable to take folic acid, vitamin B12 or corticosteroids were also excluded from the study.

The data described below reflect exposure to pemetrexed in 333 patients in PARAMOUNT. Median age was 61 years (range 32 to 83 years); 58% of patients were men; 94% were White, 4.8% were Asian, and <1% were Black or African American; 36% had an ECOG PS 0. The median number of maintenance cycles was 4 for pemetrexed and placebo arms. Dose reductions for adverse reactions occurred in 3.3% of patients in the pemetrexed arm and 0.6% in the placebo arm. Dose delays for adverse reactions occurred in 22% of patients in the pemetrexed arm and 16% in the placebo arm.

Table 6 provides the frequency and severity of adverse reactions reported in ≥5% of the 333 pemetrexed-treated patients in PARAMOUNT.

Table 6: Adverse Reactions Occurring in ≥5% of Patients Receiving Pemetrexed in PARAMOUNT
Adverse Reactiona | Pemetrexed (N=333) |  | Placebo (N=167)
Adverse Reactiona | All Grades (%) | Grade 3-4 (%) | All Grades (%) | Grades 3-4 (%)
All adverse reactions | 53 | 17 | 34 | 4.8
Laboratory
Hematologic
Anemia | 15 | 4.8 | 4.8 | 0.6
Neutropenia | 9 | 3.9 | 0.6 | 0
Clinical
Constitutional symptoms
Fatigue | 18 | 4.5 | 11 | 0.6
Gastrointestinal
Nausea | 12 | 0.3 | 2.4 | 0
Vomiting | 6 | 0 | 1.8 | 0
Mucositis/stomatitis | 5 | 0.3 | 2.4 | 0
General disorders
Edema | 5 | 0 | 3.6 | 0
a NCI CTCAE version 3.0.

The requirement for red blood cell (13% versus 4.8%) and platelet (1.5% versus 0.6%) transfusions, erythropoiesis stimulating agents (12% versus 7%), and granulocyte colony stimulating factors (6% versus 0%) were higher in the pemetrexed arm compared to the placebo arm.

The following additional Grade 3 or 4 adverse reactions were observed more frequently in the pemetrexed arm.

Incidence 1% to <5%

Blood/Bone Marrow — thrombocytopenia

General Disorders — febrile neutropenia

Incidence <1%

Cardiovascular — ventricular tachycardia, syncope

General Disorders — pain

Gastrointestinal — gastrointestinal obstruction

Neurologic — depression

Renal — renal failure

Vascular — pulmonary embolism

Treatment of Recurrent Disease After Prior Chemotherapy

The safety of pemetrexed was evaluated in Study JMEI, a randomized (1:1), open-label, active-controlled trial conducted in patients who had progressed following platinum-based chemotherapy. Patients received pemetrexed 500 mg/m^2 intravenously or docetaxel 75 mg/m^2 intravenously on Day 1 of each 21-day cycle. All patients on the pemetrexed arm received folic acid and vitamin B12 supplementation.

Study JMEI excluded patients with an ECOG PS of 3 or greater, uncontrolled third-space fluid retention, inadequate bone marrow reserve and organ function, or a calculated creatinine clearance less than 45 mL/min. Patients unable to discontinue aspirin or other non-steroidal anti-inflammatory drugs or unable to take folic acid, vitamin B12 or corticosteroids were also excluded from the study.

The data described below reflect exposure to pemetrexed in 265 patients in Study JMEI. Median age was 58 years (range 22 to 87 years); 73% of patients were men; 70% were White, 24% were Asian, 2.6% were Black or African American, 1.8% were Hispanic or Latino, and <2% were other ethnicities; 19% had an ECOG PS 0.

Table 7 provides the frequency and severity of adverse reactions reported in ≥5% of the 265 pemetrexed-treated patients in Study JMEI. Study JMEI is not designed to demonstrate a statistically significant reduction in adverse reaction rates for pemetrexed, as compared to the control arm, for any specified adverse reaction listed in the Table 7 below.

Table 7 Adverse Reactions Occurring in ≥5% of Fully Supplemented Patients Receiving Pemetrexed in Study JMEI
Adverse Reactiona | Pemetrexed (N=265) |  | Docetaxel (N=276)
Adverse Reactiona | All Grades (%) | Grades 3-4 (%) | All Grades (%) | Grades 3-4 (%)
Laboratory
Hematologic
Anemia | 19 | 4 | 22 | 4
Neutropenia | 11 | 5 | 45 | 40
Thrombocytopenia | 8 | 2 | 1 | 0
Hepatic
Increased ALT | 8 | 2 | 1 | 0
Increased AST | 7 | 1 | 1 | 0
Clinical
Gastrointestinal
Nausea | 31 | 3 | 17 | 2
Anorexia | 22 | 2 | 24 | 3
Vomiting | 16 | 2 | 12 | 1
Stomatitis/pharyngitis | 15 | 1 | 17 | 1
Diarrhea | 13 | 0 | 24 | 3
Constipation | 6 | 0 | 4 | 0
Constitutional symptoms
Fatigue | 34 | 5 | 36 | 5
Fever | 8 | 0 | 8 | 0
Dermatology/Skin
Rash/desquamation | 14 | 0 | 6 | 0
Pruritus | 7 | 0 | 2 | 0
Alopecia | 6 | 1 | 38 | 2
a NCI CTCAE version 2.0.

The following additional adverse reactions were observed in patients assigned to receive pemetrexed.

Incidence 1% to <5%

Body as a Whole — abdominal pain, allergic reaction/hypersensitivity, febrile neutropenia, infection

Dermatology/Skin — erythema multiforme

Neurology — motor neuropathy, sensory neuropathy

Incidence <1%

Cardiovascular — supraventricular arrhythmias

Renal — renal failure

Mesothelioma

The safety of pemetrexed was evaluated in Study JMCH, a randomized (1:1), single-blind study conducted in patients with MPM who had received no prior chemotherapy for MPM. Patients received pemetrexed 500 mg/m^2intravenously in combination with cisplatin 75 mg/m^2intravenously on Day 1 of each 21-day cycle or cisplatin 75 mg/m^2intravenously on Day 1 of each 21-day cycle administered until disease progression or unacceptable toxicity. Safety was assessed in 226 patients who received at least one dose of pemetrexed in combination with cisplatin and 222 patients who received at least one dose of cisplatin alone. Among 226 patients who received pemetrexed in combination with cisplatin, 74% (n=168) received full supplementation with folic acid and vitamin B12 during study therapy, 14% (n=32) were never supplemented, and 12% (n=26) were partially supplemented.

Study JMCH excluded patients with Karnofsky Performance Scale (KPS) of less than 70, inadequate bone marrow reserve and organ function, or a calculated creatinine clearance less than 45 mL/min. Patients unable to stop using aspirin or other non-steroidal anti-inflammatory drugs were also excluded from the study.

The data described below reflect exposure to pemetrexed in 168 patients that were fully supplemented with folic acid and vitamin B12. Median age was 60 years (range 19 to 85 years); 82% were men; 92% were White, 5% were Hispanic or Latino, 3.0% were Asian, and <1% were other ethnicities; 54% had KPS of 90-100. The median number of treatment cycles administered was 6 in the pemetrexed/cisplatin fully supplemented group and 2 in the pemetrexed/cisplatin never supplemented group. Patients receiving pemetrexed in the fully supplemented group had a relative dose intensity of 93% of the protocol-specified pemetrexed dose intensity. The most common adverse reaction resulting in dose delay was neutropenia.

Table 8 provides the frequency and severity of adverse reactions ≥5% in the subgroup of pemetrexed-treated patients who were fully vitamin supplemented in Study JMCH. Study JMCH was not designed to demonstrate a statistically significant reduction in adverse reaction rates for pemetrexed, as compared to the control arm, for any specified adverse reaction listed in the table below.

Table 8: Adverse Reactions Occurring in ≥5% of Fully Supplemented Subgroup of Patients Receiving Pemetrexed/Cisplatin in Study JMCHa
Adverse Reactionb | Pemetrexed /cisplatin (N=168) |  | Cisplatin (N=163)
Adverse Reactionb | All Grades (%) | Grade 3-4 (%) | All Grades (%) | Grade 3-4 (%)
Laboratory
Hematologic
Neutropenia | 56 | 23 | 13 | 3
Anemia | 26 | 4 | 10 | 0
Thrombocytopenia | 23 | 5 | 9 | 0
Renal
Elevated creatinine | 11 | 1 | 10 | 1
Decreased creatinine clearance | 16 | 1 | 18 | 2
Clinical
Eye Disorder
Conjunctivitis | 5 | 0 | 1 | 0
Gastrointestinal
Nausea | 82 | 12 | 77 | 6
Vomiting | 57 | 11 | 50 | 4
Stomatitis/pharyngitis | 23 | 3 | 6 | 0
Anorexia | 20 | 1 | 14 | 1
Diarrhea | 17 | 4 | 8 | 0
Constipation | 12 | 1 | 7 | 1
Dyspepsia | 5 | 1 | 1 | 0
Constitutional Symptoms
Fatigue | 48 | 10 | 42 | 9
Metabolism and Nutrition
Dehydration | 7 | 4 | 1 | 1
Neurology
Sensory neuropathy | 10 | 0 | 10 | 1
Taste disturbance | 8 | 0 | 6 | 0
Dermatology/Skin
Rash | 16 | 1 | 5 | 0
Alopecia | 11 | 0 | 6 | 0
a In Study JMCH, 226 patients received at least one dose of pemetrexed in combination with cisplatin and 222 patients received at least one dose of cisplatin. Table 6 provides the ADRs for subgroup of patients treated with pemetrexed in combination with cisplatin (168 patients) or cisplatin alone (163 patients) who received full supplementation with folic acid and vitamin B12 during study therapy.
b NCI CTCAE version 2.0.

The following additional adverse reactions were observed in patients receiving pemetrexed plus cisplatin:

Incidence 1% to <5%

Body as a Whole — febrile neutropenia, infection, pyrexia

Dermatology/Skin — urticaria

General Disorders — chest pain

Metabolism and Nutrition — increased AST, increased ALT, increased GGT

Renal — renal failure

Incidence <1%

Cardiovascular — arrhythmia

Neurology — motor neuropathy

Exploratory Subgroup Analyses based on Vitamin Supplementation

Table 9 provides the results of exploratory analyses of the frequency and severity of NCI CTCAE Grade 3 or 4 adverse reactions reported in more pemetrexed-treated patients who did not receive vitamin supplementation (never supplemented) as compared with those who received vitamin supplementation with daily folic acid and vitamin B12 from the time of enrollment in Study JMCH (fully-supplemented).

Table 9: Exploratory Subgroup Analysis of Selected Grade 3/4 Adverse Reactions Occurring in Patients Receiving Pemetrexed in Combination with Cisplatin with or without Full Vitamin Supplementation in Study JMCHa
Grade 3-4 Adverse Reactions | Fully Supplemented Patients N=168 (%) | Never Supplemented Patients N=32 (%)
Neutropenia | 23 | 38
Thrombocytopenia | 5 | 9
Vomiting | 11 | 31
Febrile neutropenia | 1 | 9
Infection with Grade 3/4 neutropenia | 0 | 6
Diarrhea | 4 | 9
a NCI CTCAE version 2.0.

The following adverse reactions occurred more frequently in patients who were fully vitamin supplemented than in patients who were never supplemented:

- hypertension (11% versus 3%),
- chest pain (8% versus 6%),
- thrombosis/embolism (6% versus 3%).

Additional Experience Across Clinical Trials

Sepsis, with or without neutropenia, including fatal cases: 1%

Severe esophagitis, resulting in hospitalization: <1%

6.2 Postmarketing Experience

The following adverse reactions have been identified during post-approval use of pemetrexed. Because these reactions are reported voluntarily from a population of uncertain size, it is not always possible to reliably estimate their frequency or establish a causal relationship to drug exposure.

Blood and Lymphatic System — immune-mediated hemolytic anemia

Gastrointestinal — colitis, pancreatitis

General Disorders and Administration Site Conditions — edema

Injury, poisoning, and procedural complications — radiation recall

Respiratory — interstitial pneumonitis

Skin — Serious and fatal bullous skin conditions, Stevens-Johnson syndrome, and toxic epidermal necrolysis

7 DRUG INTERACTIONS

Effects of Ibuprofen on Pemetrexed

Ibuprofen increases exposure (AUC) of pemetrexed [see Clinical Pharmacology (12.3)]. In patients with creatinine clearance between 45 mL/min and 79 mL/min:

- Avoid administration of ibuprofen for 2 days before, the day of, and 2 days following administration of AXTLE [see Dosage and Administration (2.5)].
- Monitor patients more frequently for myelosuppression, renal, and gastrointestinal toxicity, if concomitant administration of ibuprofen cannot be avoided.

8 USE IN SPECIFIC POPULATIONS

8.1 Pregnancy

Risk Summary

Based on findings from animal studies and its mechanism of action, AXTLE can cause fetal harm when administered to a pregnant woman [see Clinical Pharmacology (12.1)]. There are no available data on pemetrexed use in pregnant women. In animal reproduction studies, intravenous administration of pemetrexed to pregnant mice during the period of organogenesis was teratogenic, resulting in developmental delays and malformations at doses lower than the recommended human dose of 500 mg/m^2 [see Data]. Advise pregnant women of the potential risk to a fetus [see Use in Special Populations (8.3)].

In the U.S. general population, the estimated background risk of major birth defects and miscarriage in clinically recognized pregnancies is 2 to 4% and 15 to 20%, respectively.

Data

Animal Data

Pemetrexed was teratogenic in mice. Daily dosing of pemetrexed by intravenous injection to pregnant mice during the period of organogenesis increased the incidence of fetal malformations (cleft palate; protruding tongue; enlarged or misshaped kidney; and fused lumbar vertebra) at doses (based on BSA) 0.03 times the human dose of 500 mg/m^2. At doses, based on BSA, greater than or equal to 0.0012 times the 500 mg/m^2human dose, pemetrexed administration resulted in dose-dependent increases in developmental delays (incomplete ossification of talus and skull bone; and decreased fetal weight).

8.2 Lactation

Risk Summary

There is no information regarding the presence of pemetrexed or its metabolites in human milk, the effects on the breastfed infant, or the effects on milk production. Because of the potential for serious adverse reactions in breastfed infants from pemetrexed, advise women not to breastfeed during treatment with AXTLE and for one week after the last dose.

8.3 Females and Males of Reproductive Potential

Based on animal data, pemetrexed can cause malformations and developmental delays when administered to a pregnant woman [see Use in Specific Populations (8.1)].

Pregnancy Testing

Verify pregnancy status of females of reproductive potential prior to initiating AXTLE [see Use in Specific Populations (8.1)].

Contraception

Females

Because of the potential for genotoxicity, advise females of reproductive potential to use effective contraception during treatment with AXTLE and for 6 months after the last dose.

Males

Because of the potential for genotoxicity, advise males with female partners of reproductive potential to use effective contraception during treatment with AXTLE and for 3 months after the last dose [see Nonclinical Toxicology (13.1)].

Infertility

Males

AXTLE may impair fertility in males of reproductive potential. It is not known whether these effects on fertility are reversible [see Nonclinical Toxicology (13.1)].

8.4 Pediatric Use

The safety and effectiveness of AXTLE in pediatric patients have not been established.

The safety and pharmacokinetics of pemetrexed were evaluated in two clinical studies conducted in pediatric patients with recurrent solid tumors (NCT00070473 N=32 and NCT00520936 N=72).

Patients in both studies received concomitant vitamin B12 and folic acid supplementation and dexamethasone.

No tumor responses were observed. Adverse reactions observed in pediatric patients were similar to those observed in adults.

Single-dose pharmacokinetics of pemetrexed were evaluated in 22 patients age 4 to 18 years enrolled in NCT00070473 were within range of values in adults.

8.5 Geriatric Use

Of the 3,946 patients enrolled in clinical studies of pemetrexed, 34% were 65 and over and 4% were 75 and over. No overall differences in effectiveness were observed between these patients and younger patients. The incidences of Grade 3-4 anemia, fatigue, thrombocytopenia, hypertension, and neutropenia were higher in patients 65 years of age and older as compared to younger patients: in at least one of five randomized clinical trials. [see Adverse Reactions (6.1) and Clinical Studies (14.1, 14.2)].

8.6 Patients with Renal Impairment

Pemetrexed is primarily excreted by the kidneys. Decreased renal function results in reduced clearance and greater exposure (AUC) to pemetrexed compared with patients with normal renal function [Warnings and Precautions (5.2, 5.6) and Clinical Pharmacology (12.3)]. No dose is recommended for patients with creatinine clearance less than 45 mL/min [see Dosage and Administration (2.3)].

10 OVERDOSAGE

No drugs are approved for the treatment of pemetrexed overdose. Based on animal studies, administration of leucovorin may mitigate the toxicities of pemetrexed overdosage. It is not known whether pemetrexed is dialyzable.

11 DESCRIPTION

Pemetrexed is a folate analog metabolic inhibitor. The drug substance is pemetrexed dipotassium heptahydrate, has the chemical name L-glutamic acid, N-[4-[2-(2-amino-4,7-dihydro-4-oxo-1H-pyrrolo[2,3-d]pyrimidin-5-yl)ethyl]benzoyl]-, dipotassium salt, heptahydrate. It is a white to off-white powder having blue or green tinge with a molecular formula of C20H19K2N5O6 .7 H2O and a molecular weight of 629.49. Pemetrexed dipotassium is freely soluble in water. The reported pKaS are 3.6 and 4.5. The structural formula of pemetrexed dipotassium heptahydrate is as follows:

AXTLE is supplied as a sterile white to light-yellow or green-yellow lyophilized powder or cake for intravenous infusion available in single-dose vials. Each 100-mg or 500-mg vial of AXTLE contains 100 mg pemetrexed equivalent to 118.3 mg pemetrexed dipotassium and 106 mg mannitol or 500 mg pemetrexed equivalent to 591.5 mg pemetrexed dipotassium and 500 mg mannitol, respectively. Hydrochloric acid may have been added to adjust the pH.

12 CLINICAL PHARMACOLOGY

12.1 Mechanism of Action

Pemetrexed is a folate analog metabolic inhibitor that disrupts folate-dependent metabolic processes essential for cell replication. In vitro studies show that pemetrexed inhibits thymidylate synthase (TS), dihydrofolate reductase, and glycinamide ribonucleotide formyltransferase (GARFT), which are folate-dependent enzymes involved in the de novo biosynthesis of thymidine and purine nucleotides. Pemetrexed is taken into cells by membrane carriers such as the reduced folate carrier and membrane folate binding protein transport systems. Once in the cell, pemetrexed is converted to polyglutamate forms by the enzyme folylpolyglutamate synthetase. The polyglutamate forms are retained in cells and are inhibitors of TS and GARFT.

12.2 Pharmacodynamics

Pemetrexed inhibited the in vitro growth of mesothelioma cell lines (MSTO-211H, NCI-H2052) and showed synergistic effects when combined with cisplatin.

Based on population pharmacodynamic analyses, the depth of the absolute neutrophil counts (ANC) nadir correlates with the systemic exposure to pemetrexed and supplementation with folic acid and vitamin B12. There is no cumulative effect of pemetrexed exposure on ANC nadir over multiple treatment cycles.

12.3 Pharmacokinetics

Absorption

The pharmacokinetics of pemetrexed when pemetrexed was administered as a single agent in doses ranging from 0.2 to 838 mg/m^2infused over a 10-minute period have been evaluated in 426 cancer patients with a variety of solid tumors. Pemetrexed total systemic exposure (AUC) and maximum plasma concentration (Cmax) increased proportionally with increase of dose. The pharmacokinetics of pemetrexed did not change over multiple treatment cycles.

Distribution

Pemetrexed has a steady-state volume of distribution of 16.1 liters. In vitro studies indicated that pemetrexed is 81% bound to plasma proteins.

Elimination

The total systemic clearance of pemetrexed is 91.8 mL/min and the elimination half-life of pemetrexed is 3.5 hours in patients with normal renal function (creatinine clearance of 90 mL/min). As renal function decreases, the clearance of pemetrexed decreases and exposure (AUC) of pemetrexed increases.

Metabolism

Pemetrexed is not metabolized to an appreciable extent.

Excretion

Pemetrexed is primarily eliminated in the urine, with 70% to 90% of the dose recovered unchanged within the first 24 hours following administration. In vitro studies indicated that pemetrexed is a substrate of OAT3 (organic anion transporter 3), a transporter that is involved in the active secretion of pemetrexed.

Specific Populations

Age (26 to 80 years) and sex had no clinically meaningful effect on the systemic exposure of pemetrexed based on population pharmacokinetic analyses.

Racial Groups

The pharmacokinetics of pemetrexed were similar in Whites and Blacks or African Americans. Insufficient data are available for other ethnic groups.

Patients with Hepatic Impairment

Pemetrexed has not been formally studied in patients with hepatic impairment. No effect of elevated AST, ALT, or total bilirubin on the PK of pemetrexed was observed in clinical studies.

Patients with Renal Impairment

Pharmacokinetic analyses of pemetrexed included 127 patients with impaired renal function. Plasma clearance of pemetrexed decreases as renal function decreases, with a resultant increase in systemic exposure. Patients with creatinine clearances of 45, 50, and 80 mL/min had 65%, 54%, and 13% increases, respectively in systemic exposure (AUC) compared to patients with creatinine clearance of 100 mL/min [see Dosage and Administration (2.3) and Warnings and Precautions (5.2)].

Third-Space Fluid

The pemetrexed plasma concentrations in patients with various solid tumors with stable, mild to moderate third-space fluid were comparable to those observed in patients without third space fluid collections. The effect of severe third space fluid on pharmacokinetics is not known.

Drug Interaction Studies

Drugs Inhibiting OAT3 Transporter

Ibuprofen, an OAT3 inhibitor, administered at 400 mg four times a day decreased the clearance of pemetrexed and increased its exposure (AUC) by approximately 20% in patients with normal renal function (creatinine clearance >80 mL/min).

In Vitro Studies

Pemetrexed is a substrate for OAT3. Ibuprofen, an OAT3 inhibitor inhibited the uptake of pemetrexed in OAT3-expressing cell cultures with an average [Iµ]/IC50 ratio of 0.38. In vitro data predict that at clinically relevant concentrations, other NSAIDs (naproxen, diclofenac, celecoxib) would not inhibit the uptake of pemetrexed by OAT3 and would not increase the AUC of pemetrexed to a clinically significant extent. [see Drug Interactions (7)].

Pemetrexed is a substrate for OAT4. In vitro, ibuprofen and other NSAIDs (naproxen, diclofenac, celecoxib) are not inhibitors of OAT4 at clinically relevant concentrations.

Aspirin

Aspirin, administered in low to moderate doses (325 mg every 6 hours), does not affect the pharmacokinetics of pemetrexed.

Cisplatin

Cisplatin does not affect the pharmacokinetics of pemetrexed and the pharmacokinetics of total platinum are unaltered by pemetrexed.

Vitamins

Neither folic acid nor vitamin B12 affect the pharmacokinetics of pemetrexed.

Drugs Metabolized by Cytochrome P450 Enzymes

In vitro studies suggest that pemetrexed does not inhibit the clearance of drugs metabolized by CYP3A, CYP2D6, CYP2C9, and CYP1A2.

13 NONCLINICAL TOXICOLOGY

13.1 Carcinogenesis, Mutagenesis, Impairment of Fertility

No carcinogenicity studies have been conducted with pemetrexed. Pemetrexed was clastogenic in an in vivo micronucleus assay in mouse bone marrow but was not mutagenic in multiple in vitro tests (Ames assay, Chinese Hamster Ovary cell assay).

Pemetrexed administered intraperitoneally at doses of ≥0.1 mg/kg/day to male mice (approximately 0.0006 times the recommended human dose based on BSA) resulted in reduced fertility, hypospermia, and testicular atrophy.

14 CLINICAL STUDIES

14.1 Non-Squamous NSCLC

Initial Treatment in Combination with Pembrolizumab and Platinum

The efficacy of pemetrexed in combination with pembrolizumab and platinum chemotherapy was investigated in Study KEYNOTE-189 (NCT02578680), a randomized, multicenter, double-blind, active-controlled trial conducted in patients with metastatic non-squamous NSCLC, regardless of PD-L1 tumor expression status, who had not previously received systemic therapy for metastatic disease and in whom there were no EGFR or ALK genomic tumor aberrations. Patients with autoimmune disease that required systemic therapy within 2 years of treatment; a medical condition that required immunosuppression; or who had received more than 30 Gy of thoracic radiation within the prior 26 weeks were ineligible. Randomization was stratified by smoking status (never versus former/current), choice of platinum (cisplatin versus carboplatin), and tumor PD-L1 status (TPS <1% [negative] versus TPS ≥1%). Patients were randomized (2:1) to one of the following treatment arms:

● Pemetrexed 500 mg/m^2, pembrolizumab 200 mg, and investigator's choice of cisplatin 75 mg/m^2 or carboplatin AUC 5 mg/mL/min intravenously on Day 1 of each 21-day cycle for 4 cycles followed by pemetrexed 500 mg/m^2 and pembrolizumab 200 mg intravenously every 3 weeks. Pemetrexed was administered after pembrolizumab and prior to platinum chemotherapy on Day 1.

● Placebo, pemetrexed 500 mg/m^2, and investigator's choice of cisplatin 75 mg/m^2 or carboplatin AUC 5 mg/mL/min intravenously on Day 1 of each 21-day cycle for 4 cycles followed by placebo and pemetrexed 500 mg/m^2 intravenously every 3 weeks.

Treatment with pemetrexed continued until RECIST v1.1 (modified to follow a maximum of 10 target lesions and a maximum of 5 target lesions per organ)-defined progression of disease as determined by the investigator or unacceptable toxicity. Patients randomized to placebo, pemetrexed, and platinum chemotherapy were offered pembrolizumab as a single agent at the time of disease progression.

Assessment of tumor status was performed at Week 6, Week 12, and then every 9 weeks thereafter. The main efficacy outcome measures were OS and PFS as assessed by BICR RECIST v1.1, modified to follow a maximum of 10 target lesions and a maximum of five target lesions per organ. Additional efficacy outcome measures were ORR and duration of response, as assessed by the BICR according to RECIST v1.1, modified to follow a maximum of 10 target lesions and a maximum of 5 target lesions per organ.

A total of 616 patients were randomized: 410 patients to the pemetrexed, pembrolizumab, and platinum chemotherapy arm and 206 to the placebo, pemetrexed, and platinum chemotherapy arm. The study population characteristics were: median age of 64 years (range: 34 to 84); 49% age 65 or older; 59% male; 94% White and 3% Asian; 56% ECOG performance status of 1; and 18% with history of brain metastases. Thirty-one percent had tumor PD-L1 expression TPS <1%. Seventy-two percent received carboplatin and 12% were never smokers. A total of 85 patients in the placebo, pemetrexed, and chemotherapy arm received an anti-PD-1/PD-L1 monoclonal antibody at the time of disease progression.

The trial demonstrated a statistically significant improvement in OS and PFS for patients randomized to pemetrexed in combination with pembrolizumab and platinum chemotherapy compared with placebo, pemetrexed, and platinum chemotherapy (see Table 10 and Figure 1).

Table 10: Efficacy Results of KEYNOTE-189
Endpoint | Pemetrexed Pembrolizumab Platinum Chemotherapy n=410 | Placebo Pemetrexed Platinum Chemotherapy n=206
OS
Number (%) of patients with event | 127 (31%) | 108 (52%)
Median in months (95% CI) | NR (NR, NR) | 11.3 (8.7, 15.1)
Hazard ratioa (95% CI) | 0.49 (0.38, 0.64)
p-valueb | <0.0001
PFS
Number of patients with event (%) | 245 (60%) | 166 (81%)
Median in months (95% CI) | 8.8 (7.6, 9.2) | 4.9 (4.7, 5.5)
Hazard ratioa (95% CI) | 0.52 (0.43, 0.64)
p-valueb | <0.0001
ORR
Overall response ratec (95% CI) | 48% (43, 53) | 19% (14, 25)
Complete response | 0.5% | 0.5%
Partial response | 47% | 18%
p-valued | <0.0001
Duration of Response
Median in months (range) | 11.2 (1.1+, 18.0+) | 7.8 (2.1+, 16.4+)
a Based on the stratified Cox proportional hazard model.
b Based on stratified log-rank test.
c Response: Best objective response as confirmed complete response or partial response.
d Based on Miettinen and Nurminen method stratified by PD-L1 status, platinum chemotherapy and smoking status.
NR = not reached

At the protocol specified final OS analysis, the median in the pemetrexed in combination with pembrolizumab and platinum chemotherapy arm was 22.0 months (95% CI: 19.5, 24.5) compared to 10.6 months (95% CI: 8.7, 13.6) in the placebo with pemetrexed and platinum chemotherapy arm, with an HR of 0.56 (95% CI: 0.46, 0.69).

A+P+C = Pemetrexed + pembrolizumab + platinum chemotherapy.

A+C = Pemetrexed + platinum chemotherapy + placebo.

Figure 1: Kaplan-Meier Curve for Overall Survival in KEYNOTE-189*

*Based on the protocol-specified final OS analysis

Initial Treatment in Combination with Cisplatin

The efficacy of pemetrexed was evaluated in Study JMDB (NCT00087711), a multi-center, randomized (1:1), open-label study conducted in 1725 chemotherapy-naive patients with Stage IIIb/IV NSCLC. Patients were randomized to receive pemetrexed with cisplatin or gemcitabine with cisplatin. Randomization was stratified by Eastern Cooperative Oncology Group Performance Status (ECOG PS 0 versus 1), gender, disease stage, basis for pathological diagnosis (histopathological/cytopathological), history of brain metastases, and investigative center. Pemetrexed was administered intravenously over 10 minutes at a dose of 500 mg/m^2on Day 1 of each 21-day cycle. Cisplatin was administered intravenously at a dose of 75 mg/m^2approximately 30 minutes after pemetrexed administration on Day 1 of each cycle, gemcitabine was administered at a dose of 1250 mg/m^2on Day 1 and Day 8, and cisplatin was administered intravenously at a dose of 75 mg/m^2approximately 30 minutes after administration of gemcitabine, on Day 1 of each 21-day cycle. Treatment was administered up to a total of 6 cycles; patients in both arms received folic acid, vitamin B12, and dexamethasone [see Dosage and Administration (2.4)]. The primary efficacy outcome measure was overall survival.

A total of 1725 patients were enrolled with 862 patients randomized to pemetrexed in combination with cisplatin and 863 patients to gemcitabine in combination with cisplatin. The median age was 61 years (range 26-83 years), 70% were male, 78% were White, 17% were Asian, 2.9% were Hispanic or Latino, and 2.1% were Black or African American, and <1% were other ethnicities. Among patients for whom ECOG PS (n=1722) and smoking history (n=1516) were collected, 65% had an ECOG PS of 1, 36% had an ECOG PS of 0, and 84% were smokers. For tumor characteristics, 73% had non-squamous NSCLC and 27% had squamous NSCLC; 76% had Stage IV disease. Among 1252 patients with non-squamous NSCLC histology, 68% had a diagnosis of adenocarcinoma, 12% had large cell histology and 20% had other histologic subtypes.

Efficacy results in Study JMDB are presented in Table 11 and Figure 2.

Table 11: Efficacy Results in Study JMDB
Efficacy Parameter | Pemetrexed plus Cisplatin (N=862) | Gemcitabine plus Cisplatin (N=863)
Overall Survival
Median (months) (95% CI) | 10.3 (9.8-11.2) | 10.3 (9.6-10.9)
Hazard ratio (HR)a,b (95% CI) | 0.94 (0.84-1.05)
Progression-Free Survival
Median (months) (95% CI) | 4.8 (4.6-5.3) | 5.1 (4.6-5.5)
Hazard ratio (HR)a,b (95% CI) | 1.04 (0.94-1.15)
Overall Response Rate (95% CI) | 27.1% (24.2-30.1) | 24.7% (21.8-27.6)
a Unadjusted for multiple comparisons.
b Adjusted for gender, stage, basis of diagnosis, and performance status.

In pre-specified analyses assessing the impact of NSCLC histology on overall survival, clinically relevant differences in survival according to histology were observed. These subgroup analyses are shown in Table 12 and Figures 3 and 4. This difference in treatment effect for pemetrexed based on histology demonstrating a lack of efficacy in squamous cell histology was also observed in Studies JMEN and JMEI.

Table 12: Overall Survival in NSCLC Histologic Subgroups in Study JMDB
Histologic Subgroups | Pemetrexed plus Cisplatin (N=862) | Gemcitabine plus Cisplatin (N=863)
Non-squamous NSCLC (N=1252)
Median (months) (95% CI) | 11.0 (10.1-12.5) | 10.1 (9.3-10.9)
HRa,b (95% CI) | 0.84 (0.74-0.96)
Adenocarcinoma (N=847)
Median (months) (95% CI) | 12.6 (10.7-13.6) | 10.9 (10.2-11.9)
HRa,b (95% CI) | 0.84 (0.71-0.99)
Large Cell (N=153)
Median (months) (95% CI) | 10.4 (8.6-14.1) | 6.7 (5.5-9.0)
HRa,b (95% CI) | 0.67 (0.48-0.96)
Non-squamous, not otherwise specified (N=252)
Median (months) (95% CI) | 8.6 (6.8-10.2) | 9.2 (8.1-10.6)
HRa,b (95% CI) | 1.08 (0.81-1.45)
Squamous Cell (N=473)
Median (months) (95% CI) | 9.4 (8.4-10.2) | 10.8 (9.5-12.1)
HRa,b (95% CI) | 1.23 (1.00-1.51)
a Unadjusted for multiple comparisons.
b Adjusted for ECOG PS, gender, disease stage, and basis for pathological diagnosis (histopathological/cytopathological).

Maintenance Treatment Following First-line Non-Pemetrexed Containing Platinum-Based Chemotherapy

The efficacy of pemetrexed as maintenance therapy following first-line platinum-based chemotherapy was evaluated in Study JMEN (NCT00102804), a multicenter, randomized (2:1), double-blind, placebo-controlled study conducted in 663 patients with Stage IIIb/IV NSCLC who did not progress after four cycles of platinum-based chemotherapy. Patients were randomized to receive pemetrexed 500 mg/m^2intravenously every 21 days or placebo until disease progression or intolerable toxicity. Patients in both study arms received folic acid, vitamin B12, and dexamethasone [see Dosage and Administration (2.4)]. Randomization was carried out using a minimization approach [Pocock and Simon (1975)] using the following factors: gender, ECOG PS (0 versus 1), response to prior chemotherapy (complete or partial response versus stable disease), history of brain metastases (yes versus no), non-platinum component of induction therapy (docetaxel versus gemcitabine versus paclitaxel), and disease stage (IIIb versus IV). The major efficacy outcome measures were progression-free survival based on assessment by independent review and overall survival; both were measured from the date of randomization in Study JMEN.

A total of 663 patients were enrolled with 441 patients randomized to pemetrexed and 222 patients randomized to placebo. The median age was 61 years (range 26-83 years); 73% were male; 65% were White, 32% were Asian, 2.9% were Hispanic or Latino, and <2% were other ethnicities; 60% had an ECOG PS of 1; and 73% were current or former smokers. Median time from initiation of platinum-based chemotherapy to randomization was 3.3 months (range 1.6 to 5.1 months) and 49% of the population achieved a partial or complete response to first-line, platinum-based chemotherapy. With regard to tumor characteristics, 81% had Stage IV disease, 73% had non-squamous NSCLC and 27% had squamous NSCLC. Among the 481 patients with non-squamous NSCLC, 68% had adenocarcinoma, 4% had large cell, and 28% had other histologies.

Efficacy results are presented in Table 13 and Figure 5.

Table 13: Efficacy Results in Study JMEN
Efficacy Parameter | Pemetrexed | Placebo
Overall survival | N=441 | N=222
Median (months) (95% CI) | 13.4 (11.9-15.9) | 10.6 (8.7-12.0)
Hazard ratioa (95% CI) | 0.79 (0.65-0.95)
p-value | p=0.012
Progression-free survival per independent review | N=387 | N=194
Median (months) (95% CI) | 4.0 (3.1-4.4) | 2.0 (1.5-2.8)
Hazard ratioa (95% CI) | 0.60 (0.49-0.73)
p-value | p<0.00001
a Hazard ratios are adjusted for multiplicity but not for stratification variables.

The results of pre-specified subgroup analyses by NSCLC histology are presented in Table 14 and Figures 6 and 7.

Table 14: Efficacy Results in Study JMEN by Histologic Subgroup
Efficacy Parameter | Overall Survival |  | Progression-Free Survival Per Independent Review
Efficacy Parameter | Pemetrexed (N=441) | Placebo (N=222) | Pemetrexed (N=387) | Placebo (N=194)
Non-squamous NSCLC (n=481)
Median (months) | 15.5 | 10.3 | 4.4 | 1.8
HRa (95% CI) | 0.70 (0.56-0.88) |  | 0.47 (0.37-0.60)
Adenocarcinoma (n=328)
Median (months) | 16.8 | 11.5 | 4.6 | 2.7
HRa (95% CI) | 0.73 (0.56-0.96) |  | 0.51 (0.38-0.68)
Large cell carcinoma (n=20)
Median (months) | 8.4 | 7.9 | 4.5 | 1.5
HRa (95% CI) | 0.98 (0.36-2.65) |  | 0.40 (0.12-1.29)
Otherb (n=133)
Median (months) | 11.3 | 7.7 | 4.1 | 1.6
HRa (95% CI) | 0.61 (0.40-0.94) |  | 0.44 (0.28-0.68)
Squamous cell NSCLC (n=182)
Median (months) | 9.9 | 10.8 | 2.4 | 2.5
HRa (95% CI) | 1.07 (0.77-1.50) |  | 1.03 (0.71-1.49)
a Hazard ratios are not adjusted for multiplicity
b Primary diagnosis of NSCLC not specified as adenocarcinoma, large cell carcinoma, or squamous cell carcinoma.

Maintenance Treatment Following First-line Pemetrexed Plus Platinum Chemotherapy

The efficacy of pemetrexed as maintenance therapy following first-line platinum-based chemotherapy was also evaluated in PARAMOUNT (NCT00789373), a multi-center, randomized (2:1), double-blind, placebo-controlled study conducted in patients with Stage IIIb/IV non-squamous NSCLC who had completed four cycles of pemetrexed in combination with cisplatin and achieved a complete response (CR) or partial response (PR) or stable disease (SD). Patients were required to have an ECOG PS of 0 or 1. Patients were randomized to receive pemetrexed 500 mg/m^2intravenously every 21 days or placebo until disease progression. Randomization was stratified by response to pemetrexed in combination with cisplatin induction therapy (CR or PR versus SD), disease stage (IIIb versus IV), and ECOG PS (0 versus 1). Patients in both arms received folic acid, vitamin B12, and dexamethasone. The main efficacy outcome measure was investigator-assessed progression-free survival (PFS) and an additional efficacy outcome measure was overall survival (OS); PFS and OS were measured from the time of randomization.

A total of 539 patients were enrolled with 359 patients randomized to pemetrexed and 180 patients randomized to placebo. The median age was 61 years (range 32 to 83 years); 58% were male; 95% were White, 4.5% were Asian, and <1% were Black or African American; 67% had an ECOG PS of 1; 78% were current or former smokers; and 43% of the population achieved a partial or complete response to first-line, platinum-based chemotherapy. With regard to tumor characteristics, 91% had Stage IV disease, 87% had adenocarcinoma, 7% had large cell, and 6% had other histologies.

Efficacy results for PARAMOUNT are presented in Table 15 and Figure 8.

Table 15: Efficacy Results in PARAMOUNT
Efficacy Parameter | Pemetrexed (N=359) | Placebo (N=180)
Overall survival
Median (months) (95% CI) | 13.9 (12.8-16.0) | 11.0 (10.0-12.5)
Hazard ratio (HR)a (95% CI) | 0.78 (0.64-0.96)
p-value | p=0.02
Progression-free survivalb
Median (months) (95% CI) | 4.1 (3.2-4.6) | 2.8 (2.6-3.1)
Hazard ratio (HR)a (95% CI) | 0.62 (0.49-0.79)
p-value | p<0.0001
a Hazard ratios are adjusted for multiplicity but not for stratification variables.
b Based on investigator's assessment.

Treatment of Recurrent Disease After Prior Chemotherapy

The efficacy of pemetrexed was evaluated in Study JMEI (NCT00004881), a multicenter, randomized (1:1), open-label study conducted in patients with Stage III or IV NSCLC that had recurred or progressed following one prior chemotherapy regimen for advanced disease. Patients were randomized to receive pemetrexed 500 mg/m^2intravenously or docetaxel 75 mg/m^2as a 1-hour intravenous infusion once every 21 days. Patients randomized to pemetrexed also received folic acid and vitamin B12. The study was designed to show that overall survival with pemetrexed was non-inferior to docetaxel, as the major efficacy outcome measure, and that overall survival was superior for patients randomized to pemetrexed compared to docetaxel, as a secondary outcome measure.

A total of 571 patients were enrolled with 283 patients randomized to pemetrexed and 288 patients randomized to docetaxel. The median age was 58 years (range 22 to 87 years); 72% were male; 71% were White, 24% were Asian, 2.8% were Black or African American, 1.8% were Hispanic or Latino, and <2% were other ethnicities; 88% had an ECOG PS of 0 or

1. With regard to tumor characteristics, 75% had Stage IV disease; 53% had adenocarcinoma, 30% had squamous histology; 8% large cell; and 9% had other histologic subtypes of NSCLC.

The efficacy results in the overall population and in subgroup analyses based on histologic subtype are provided in Tables 16 and 17, respectively. Study JMEI did not show an improvement in overall survival in the intent-to-treat population. In subgroup analyses, there was no evidence of a treatment effect on survival in patients with squamous NSCLC; the absence of a treatment effect in patients with NSCLC of squamous histology was also observed Studies JMDB and JMEN [see Clinical Studies (14.1)].

Table 16: Efficacy Results in Study JMEI
Efficacy Parameter | Pemetrexed (N=283) | Docetaxel (N=288)
Overall survival
Median (months) (95% CI) | 8.3 (7.0-9.4) | 7.9 (6.3-9.2)
Hazard ratioa (95% CI) | 0.99 (0.82-1.20)
Progression-free survival
Median (months) (95% CI) | 2.9 (2.4-3.1) | 2.9 (2.7-3.4)
Hazard ratioa (95% CI) | 0.97 (0.82-1.16)
Overall response rate (95% CI) | 8.5% (5.2-11.7) | 8.3% (5.1-11.5)
a Hazard ratios are not adjusted for multiplicity or for stratification variables.

Table 17: Exploratory Efficacy Analyses by Histologic Subgroup in Study JMEI
Histologic Subgroups | Pemetrexed (N=283) | Docetaxel (N=288)
Non-squamous NSCLC (N=399)
Median (months) (95% CI) | 9.3 (7.8-9.7) | 8.0 (6.3-9.3)
HRa (95% CI) | 0.89 (0.71-1.13)
Adenocarcinoma (N=301)
Median (months) (95% CI) | 9.0 (7.6-9.6) | 9.2 (7.5-11.3)
HRa (95% CI) | 1.09 (0.83-1.44)
Large Cell (N=47)
Median (months) (95% CI) | 12.8 (5.8-14.0) | 4.5 (2.3-9.1)
HRa (95% CI) | 0.38 (0.18-0.78)
Otherb (N=51)
Median (months) (95% CI) | 9.4 (6.0-10.1) | 7.9 (4.0-8.9)
HRa (95% CI) | 0.62 (0.32-1.23)
Squamous NSCLC (N=172)
Median (months) (95% CI) | 6.2 (4.9-8.0) | 7.4 (5.6-9.5)
HRa (95% CI) | 1.32 (0.93-1.86)
a Hazard ratio unadjusted for multiple comparisons.
b Primary diagnosis of NSCLC not specified as adenocarcinoma, large cell carcinoma, or squamous cell carcinoma.

14.2 Mesothelioma

The efficacy of pemetrexed was evaluated in Study JMCH (NCT00005636), a multicenter, randomized (1:1), single-blind study conducted in patients with MPM who had received no prior chemotherapy. Patients were randomized (n=456) to receive pemetrexed 500 mg/m^2intravenously over 10 minutes followed 30 minutes later by cisplatin 75 mg/m^2intravenously over two hours on Day 1 of each 21-day cycle or to receive cisplatin 75 mg/m^2intravenously over 2 hours on Day 1 of each 21-day cycle; treatment continued until disease progression or intolerable toxicity. The study was modified after randomization and treatment of 117 patients to require that all patients receive folic acid 350 mcg to 1000 mcg daily beginning 1 to 3 weeks prior to the first dose of pemetrexed and continuing until 1 to 3 weeks after the last dose, vitamin B12 1000 mcg intramuscularly 1 to 3 weeks prior to first dose of pemetrexed and every 9 weeks thereafter, and dexamethasone 4 mg orally, twice daily, for 3 days starting the day prior to each pemetrexed dose. Randomization was stratified by multiple baseline variables including KPS, histologic subtype (epithelial, mixed, sarcomatoid, other), and gender. The major efficacy outcome measure was overall survival and additional efficacy outcome measures were time to disease progression, overall response rate, and response duration.

A total of 448 patients received at least one dose of protocol-specified therapy; 226 patients were randomized to and received at least one dose of pemetrexed plus cisplatin, and 222 patients were randomized to and received cisplatin. Among the 226 patients who received cisplatin with pemetrexed, 74% received full supplementation with folic acid and vitamin B12 during study therapy, 14% were never supplemented, and 12% were partially supplemented. Across the study population, the median age was 61 years (range: 20 to 86 years); 81% were male; 92% were White, 5% were Hispanic or Latino, 3.1% were Asian, and <1% were other ethnicities; and 54% had a baseline KPS score of 90-100% and 46% had a KPS score of 70-80%. With regard to tumor characteristics, 46% had Stage IV disease, 31% Stage III, 15% Stage II, and 7% Stage I disease at baseline; the histologic subtype of mesothelioma was epithelial in 68% of patients, mixed in 16%, sarcomatoid in 10% and other histologic subtypes in 6%. The baseline demographics and tumor characteristics of the subgroup of fully supplemented patients was similar to the overall study population.

The efficacy results from Study JMCH are summarized in Table 18 and Figure 9.

Table 18: Efficacy Results in Study JMCH
Efficacy Parameter | All Randomized and Treated Patients (N=448) |  | Fully Supplemented Patients (N=331)
Efficacy Parameter | Pemetrexed /Cisplatin (N=226) | Cisplatin (N=222) | Pemetrexed /Cisplatin (N=168) | Cisplatin (N=163)
Median overall survival (months) | 12.1 | 9.3 | 13.3 | 10.0
(95% CI) | (10.0-14.4) | (7.8-10.7) | (11.4-14.9) | (8.4-11.9)
Hazard ratioa | 0.77 |  | 0.75
Log rank p-value | 0.020 |  | NAb
a Hazard ratios are not adjusted for stratification variables.
b Not a pre-specified analysis.

Based upon prospectively defined criteria (modified Southwest Oncology Group methodology) the objective tumor response rate for pemetrexed plus cisplatin was greater than the objective tumor response rate for cisplatin alone. There was also improvement in lung function (forced vital capacity) in the pemetrexed plus cisplatin arm compared to the control arm.

15 REFERENCES

1. "OSHA Hazardous Drugs." OSHA. [https://www.osha.gov/hazardous-drugs]

16 HOW SUPPLIED/STORAGE AND HANDLING

How Supplied

AXTLETM, is a sterile preservative free white-to-light yellow or green-yellow lyophilized powder supplied in single-dose vials for reconstitution for intravenous infusion.

NDC 83831-131-01: 100 mg single-dose vial containing pemetrexed equivalent to 118.3 mg pemetrexed dipotassium with aluminum flip-off seals with grey color button individually packaged in a carton.

NDC 83831-132-01: 500 mg single-dose vial containing pemetrexed equivalent to 591.5 mg pemetrexed dipotassium with aluminum flip-off seals with red color button individually packaged in a carton.

Storage and Handling

Store at controlled room temperature, 20°C to 25°C (68°F to 77°F); excursions permitted from 15°C to 30°C (59°F to 86°F) [see USP Controlled Room Temperature].

AXTLE is a hazardous drug. Follow applicable special handling and disposal procedures.^1

17 PATIENT COUNSELING INFORMATION

Advise the patient to read the FDA-approved patient labeling (Patient Information).

Premedication and Concomitant Medication: Instruct patients to take folic acid as directed and to keep appointments for vitamin B12 injections to reduce the risk of treatment-related toxicity. Instruct patients of the requirement to take corticosteroids to reduce the risks of treatment-related toxicity [see Dosage and Administration (2.4) and Warnings and Precautions (5.1)].

Myelosuppression: Inform patients of the risk of low blood cell counts and instruct them to immediately contact their physician for signs of infection, fever, bleeding, or symptoms of anemia [see Warnings and Precautions (5.1)].

Renal Failure: Inform patients of the risks of renal failure, which may be exacerbated in patients with dehydration arising from severe vomiting or diarrhea. Instruct patients to immediately contact their healthcare provider for a decrease in urine output [see Warnings and Precautions (5.2)].

Bullous and Exfoliative Skin Disorders: Inform patients of the risks of severe and exfoliative skin disorders. Instruct patients to immediately contact their healthcare provider for development of bullous lesions or exfoliation in the skin or mucous membranes [see Warnings and Precautions (5.3)].

Interstitial Pneumonitis: Inform patients of the risks of pneumonitis. Instruct patients to immediately contact their healthcare provider for development of dyspnea or persistent cough [see Warnings and Precautions (5.4)].

Radiation Recall: Inform patients who have received prior radiation of the risks of radiation recall. Instruct patients to immediately contact their healthcare provider for development of inflammation or blisters in an area that was previously irradiated [see Warnings and Precautions (5.5)].

Increased Risk of Toxicity with Ibuprofen in Patients with Renal Impairment: Advise patients with mild to moderate renal impairment of the risks associated with concomitant ibuprofen use and instruct them to avoid use of all ibuprofen containing products for 2 days before, the day of, and 2 days following administration of AXTLE [see Dosage and Administration (2.5), Warnings and Precautions (5.6), and Drug Interactions (7)].

Embryo-Fetal Toxicity: Advise females of reproductive potential and males with female partners of reproductive potential of the potential risk to a fetus [see Warnings and Precautions (5.7) and Use in Specific Populations (8.1)]. Advise females of reproductive potential to use effective contraception during treatment with AXTLE and for 6 months after the last dose. Advise females to inform their prescriber of a known or suspected pregnancy. Advise males with female partners of reproductive potential to use effective contraception during treatment with AXTLE and for 3 months after the last dose [see Warnings and Precautions (5.7) and Use in Specific Populations (8.3)].

Lactation: Advise women not to breastfeed during treatment with AXTLE and for 1 week after the last dose [see Use in Specific Populations (8.2)].

Manufactured for:

Avyxa Pharma, LLC

New Jersey 07054, USA

Made in India

SPL PATIENT PACKAGE INSERT

PATIENT INFORMATION
AXTLETM (AXE-tul)
(pemetrexed) for injection
for intravenous use

What is AXTLE?
AXTLE is a prescription medicine used to treat:
● a kind of lung cancer called non-squamous non-small cell lung cancer (NSCLC).
AXTLE is used:
○ as the first treatment in combination with pembrolizumab and platinum chemotherapy when your lung cancer with no abnormal EGFR or ALK gene has spread (advanced NSCLC).
○ as the first treatment in combination with cisplatin when your lung cancer has spread (advanced NSCLC).
○ alone as maintenance treatment after you have received 4 cycles of chemotherapy that contains platinum for first treatment of your advanced NSCLC and your cancer has not progressed.
● alone when your lung cancer has returned or spread after prior chemotherapy.
AXTLE is not for use for the treatment of people with squamous cell non-small cell lung cancer.
● a kind of cancer called malignant pleural mesothelioma. This cancer affects the lining of the lungs and chest wall. AXTLE is used in combination with cisplatin as the first treatment for malignant pleural mesothelioma that cannot be removed by surgery or you are not able to have surgery.
AXTLE has not been shown to be safe and effective in children.

Do not take AXTLE : if you have had a severe allergic reaction to any medicine that contains pemetrexed.

Before taking AXTLE, tell your healthcare provider about all of your medical conditions, including if you:
● have kidney problems.
● have had radiation therapy.
● are pregnant or plan to become pregnant . AXTLE can harm your unborn baby.
Females who are able to become pregnant :
Your healthcare provider will check to see if you are pregnant before you start treatment with AXTLE.
You should use effective birth control (contraception) during treatment with AXTLE and for 6 months after the last dose. Tell your healthcare provider right away if you become pregnant or think you are pregnant during treatment with AXTLE.
Males with female partners who are able to become pregnant should use effective birth control (contraception) during treatment with AXTLE and for 3 months after the last dose.
● are breastfeeding or plan to breastfeed . It is not known if AXTLE passes into breast milk. Do not breastfeed during treatment with AXTLE and for 1 week after the last dose.
Tell your healthcare provider about all the medicines you take, including prescription and over-the-counter medicines, vitamins, and herbal supplements.
Tell your healthcare provider if you have kidney problems and take a medicine that contains ibuprofen . You should avoid taking ibuprofen for 2 days before, the day of, and 2 days after receiving treatment with AXTLE.

How is AXTLE given?
● It is very important to take folic acid and vitamin B12 during your treatment with AXTLE to lower your risk of harmful side effects.
○ Take folic acid exactly as prescribed by your healthcare provider 1 time a day, beginning 7 days (1 week) before your first dose of AXTLE and continue taking folic acid until 21 days (3 weeks) after your last dose of AXTLE.
○ Your healthcare provider will give you vitamin B12 injections during treatment with AXTLE. You will get your first vitamin B12 injection 7 days (1 week) before your first dose of AXTLE, and then every 3 cycles.
● Your healthcare provider will prescribe a medicine called corticosteroid for you to take 2 times a day for 3 days, beginning the day before each treatment with AXTLE.
● AXTLE is given to you by intravenous (IV) infusion into your vein. The infusion is given over 10 minutes.
● AXTLE is usually given once every 21 days (3 weeks).

What are the possible side effects of AXTLE?
AXTLE can cause serious side effects, including:
● Low blood cell counts. Low blood cell counts can be severe, including low white blood cell counts (neutropenia), low platelet counts (thrombocytopenia), and low red blood cell counts (anemia). Your healthcare provider will do blood tests to check your blood cell counts regularly during your treatment with AXTLE. Tell your healthcare provider right away if you have any signs of infection, fever, bleeding, or severe tiredness during your treatment with AXTLE.
● Kidney problems, including kidney failure. AXTLE can cause severe kidney problems that can lead to death. Severe vomiting or diarrhea can lead to loss of fluids (dehydration) which may cause kidney problems to become worse. Tell your healthcare provider right away if you have a decrease in amount of urine.
● Severe skin reactions. Severe skin reactions that may lead to death can happen with AXTLE. Tell your healthcare provider right away if you develop blisters, skin sores, skin peeling, or painful sores, or ulcers in your mouth, nose, throat or genital area.
● Lung problems (pneumonitis). AXTLE can cause serious lung problems that can lead to death. Tell your healthcare provider right away if you get any new or worsening symptoms of shortness of breath, cough, or fever.
● Radiation recall. Radiation recall is a skin reaction that can happen in people who have received radiation treatment in the past and are treated with AXTLE. Tell your healthcare provider if you get swelling, blistering, or a rash that looks like a sunburn in an area that was previously treated with radiation.
The most common side effects of AXTLE when given alone are:
● tiredness ● nausea ● loss of appetite
The most common side effects of AXTLE when given with cisplatin are:

● vomiting
● swelling or sores in your mouth or sore throat
● constipation

● low white blood cell counts (neutropenia)
● low platelet counts (thrombocytopenia)
● low red blood cell counts (anemia)

The most common side effects of AXTLE when given with pembrolizumab and platinum chemotherapy are:

● tiredness and weakness
● constipation
● loss of appetite
● vomiting
● shortness of breath

● nausea
● diarrhea
● rash
● cough
● fever

AXTLE may cause fertility problems in males. This may affect your ability to father a child. It is not known if these effects are reversible. Talk to your healthcare provider if this is a concern for you.
Your healthcare provider will do blood tests to check for side effects during treatment with AXTLE. Your healthcare provider may change your dose of AXTLE, delay treatment, or stop treatment if you have certain side effects.
Tell your healthcare provider if you have any side effect that bothers you or that does not go away.
These are not all the side effects of AXTLE. For more information, ask your healthcare provider or pharmacist.
Call your doctor for medical advice about side effects. You may report side effects to FDA at
1-800-FDA-1088.

General information about the safe and effective use of AXTLE.
Medicines are sometimes prescribed for purposes other than those listed in a Patient Information leaflet.
You can ask your pharmacist or healthcare provider for information about AXTLE that is written for health professionals.

What are the ingredients in AXTLE?
Active ingredient: pemetrexed
Inactive ingredients: mannitol. Hydrochloric acid may have been added to adjust pH.

Manufactured for:
Avyxa Pharma, LLC
New Jersey 07054, USA
Made in India
For more information, call 1-888-520-0954.

This Patient Information has been approved by the U.S. Food and Drug Administration. Issued: October 2025

PACKAGE LABEL.PRINCIPAL DISPLAY PANEL

Axtle (Pemetrexed) for Injection -Container Label- -100mg/vial
Axtle (Pemetrexed) for Injection -Carton Label -100mg/vial
Axtle (Pemetrexed) for Injection -Container Label- -500mg/vial
Axtle (Pemetrexed) for Injection -Carton Label -500mg/vial